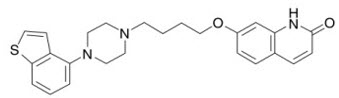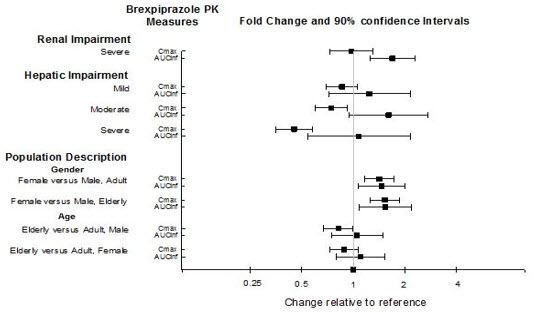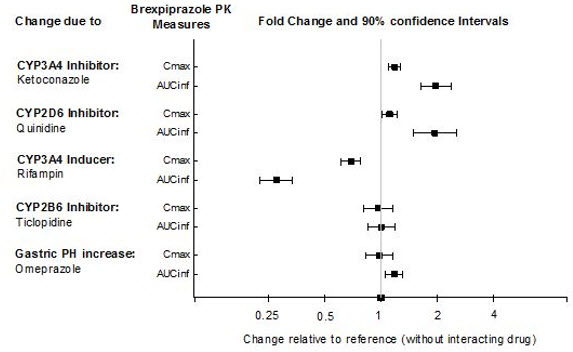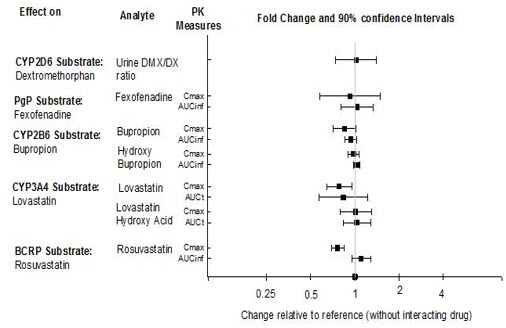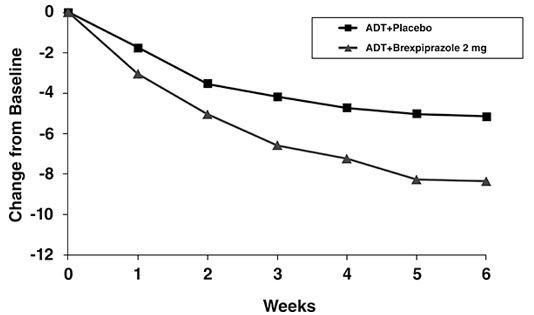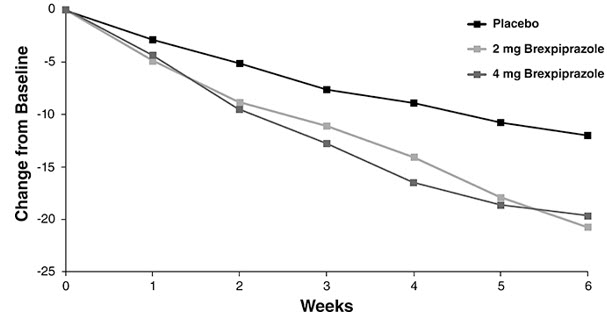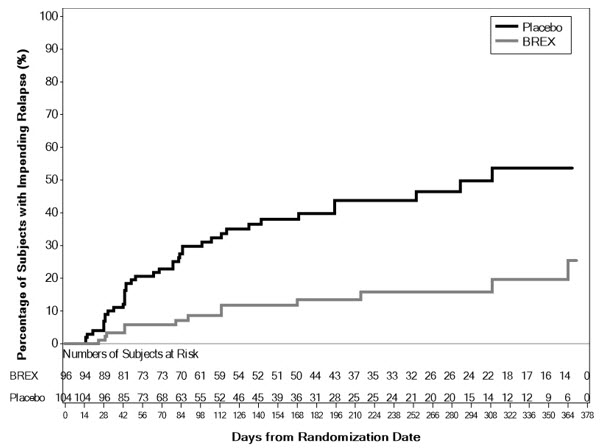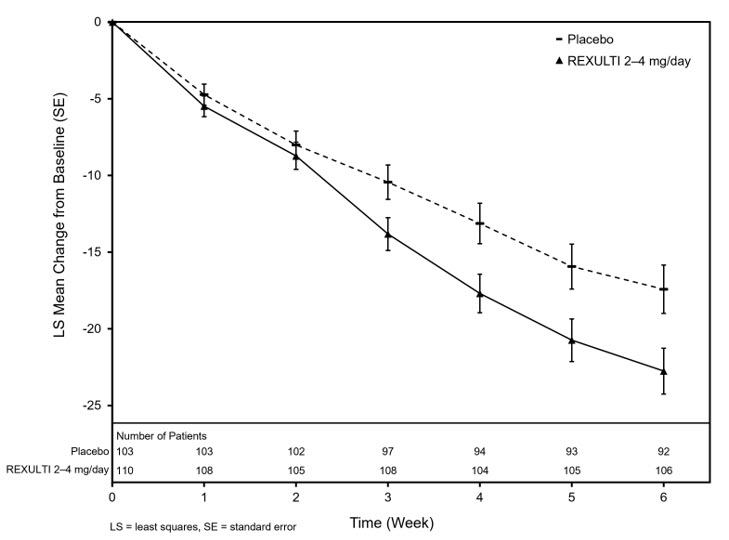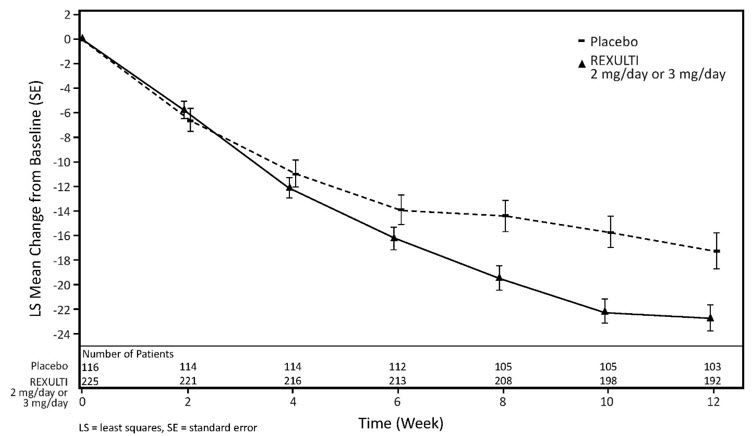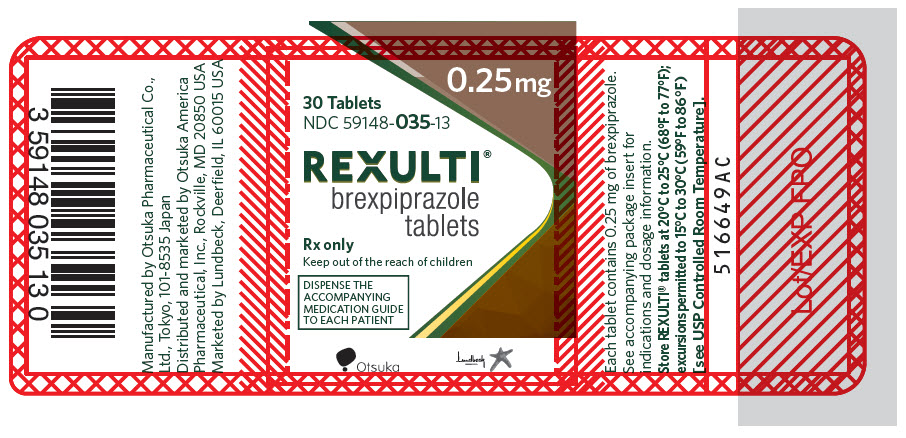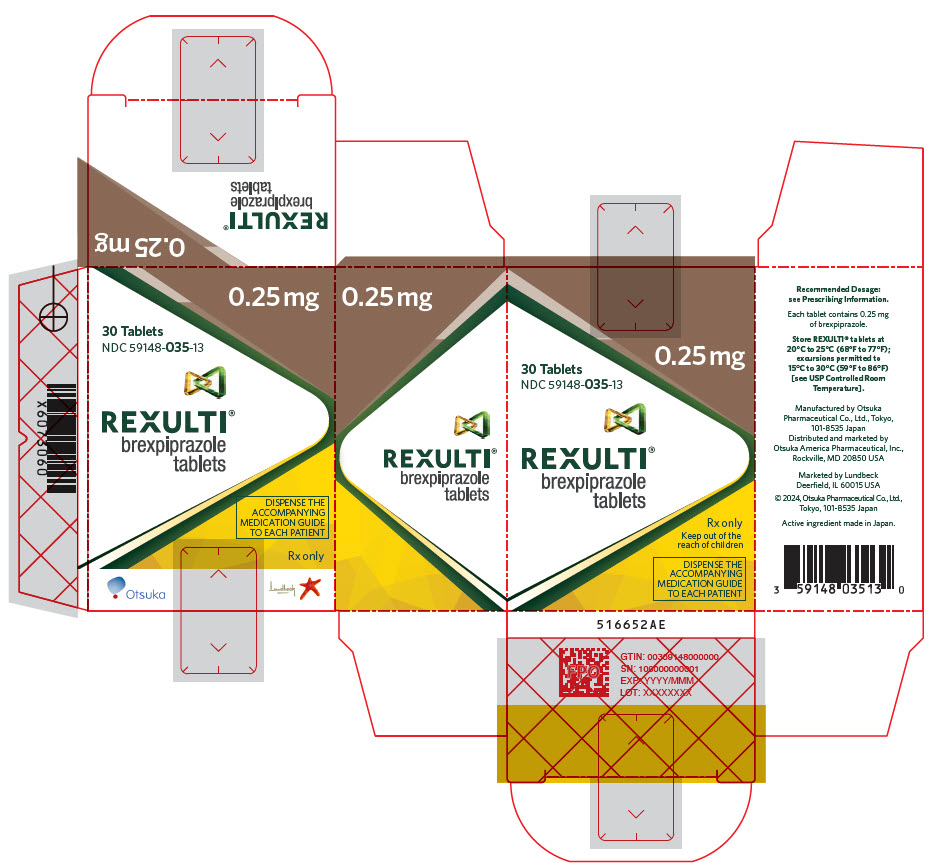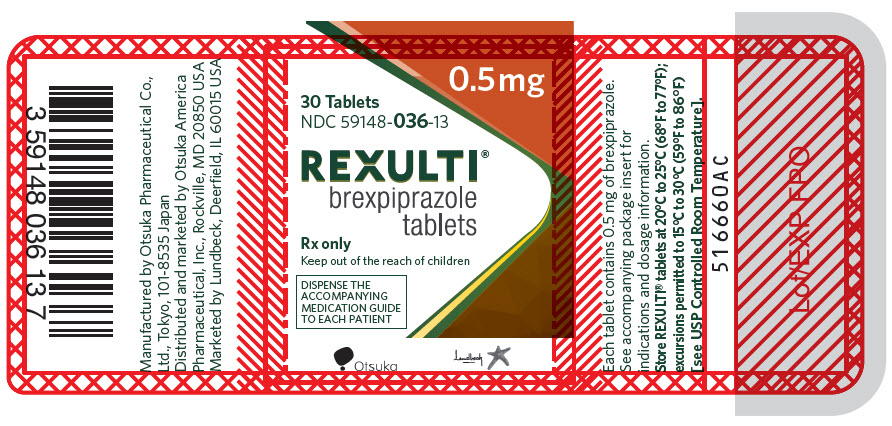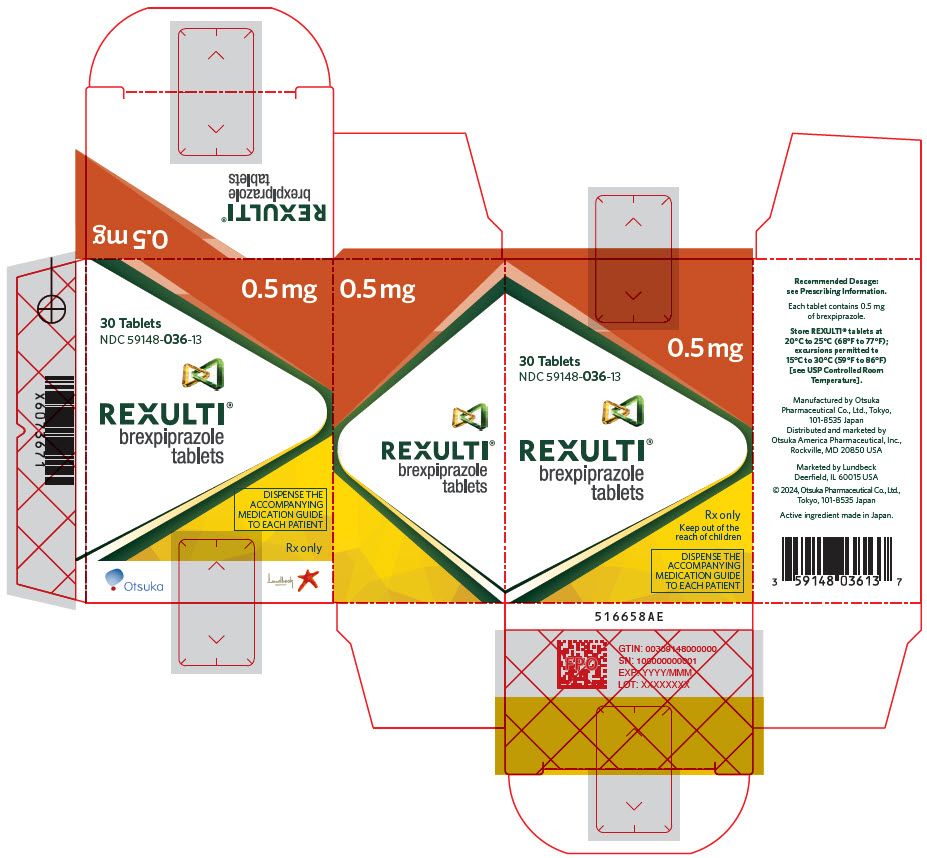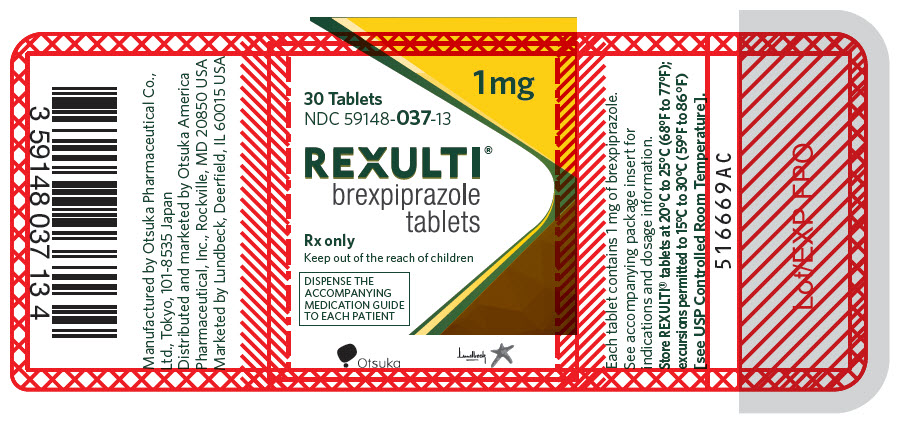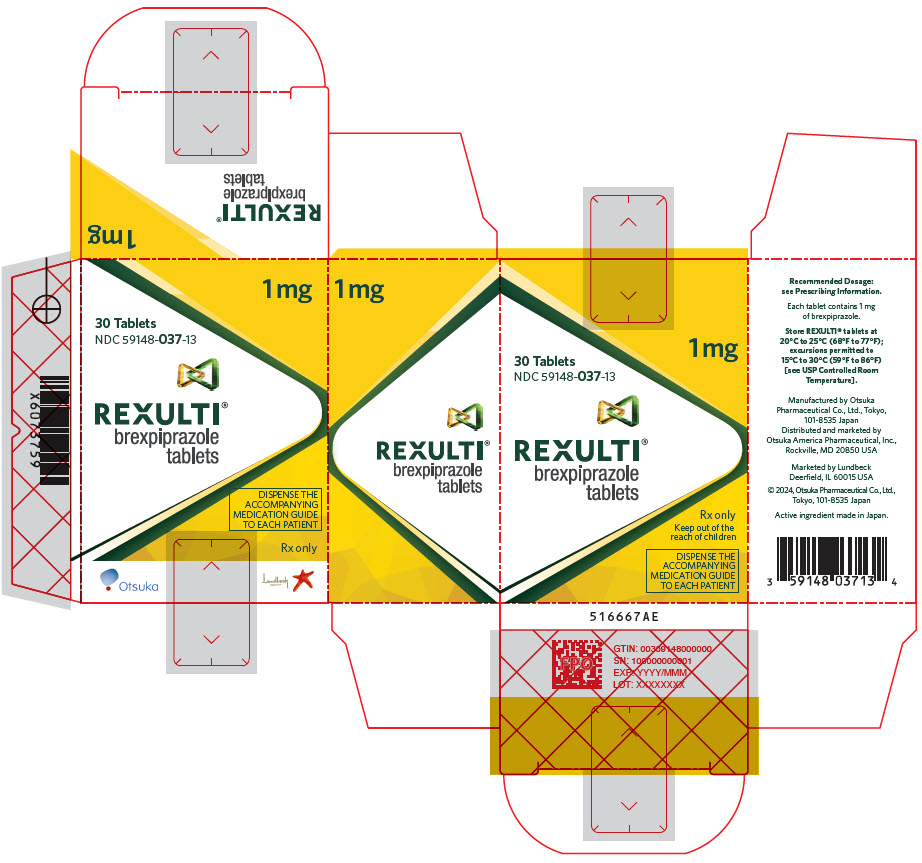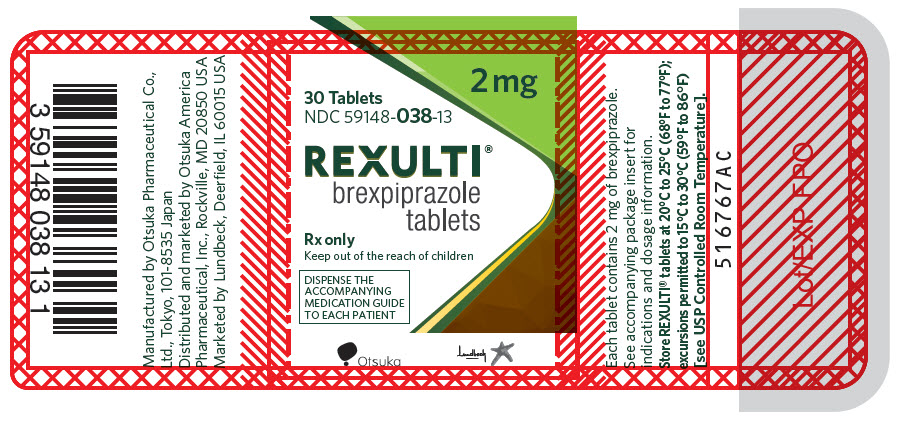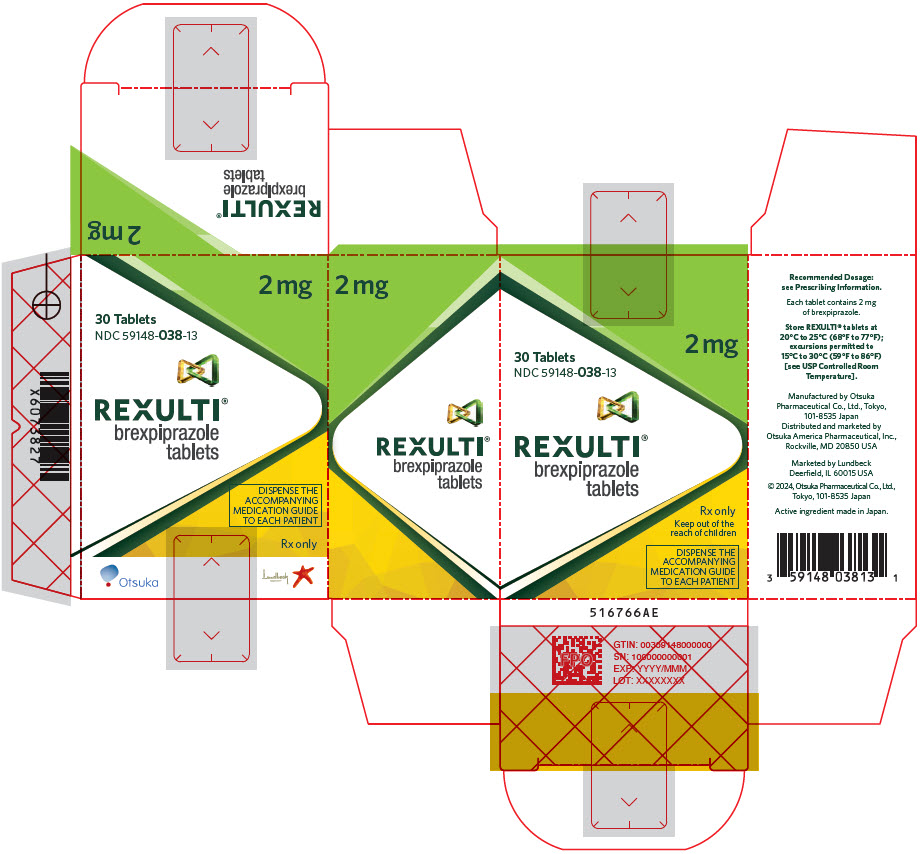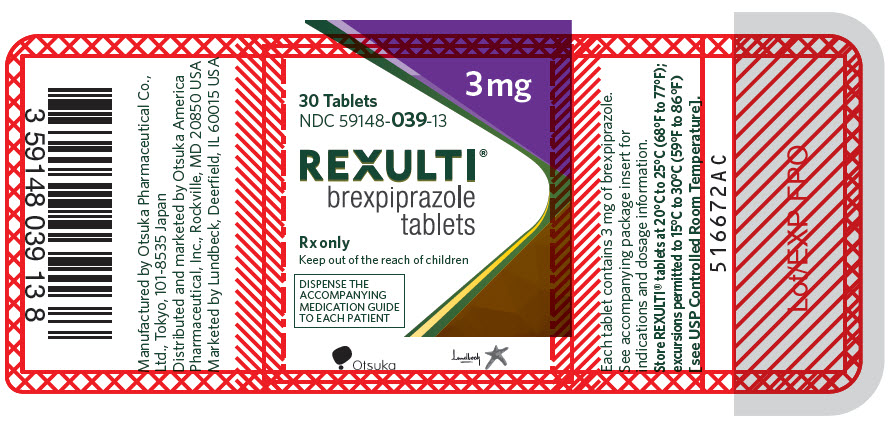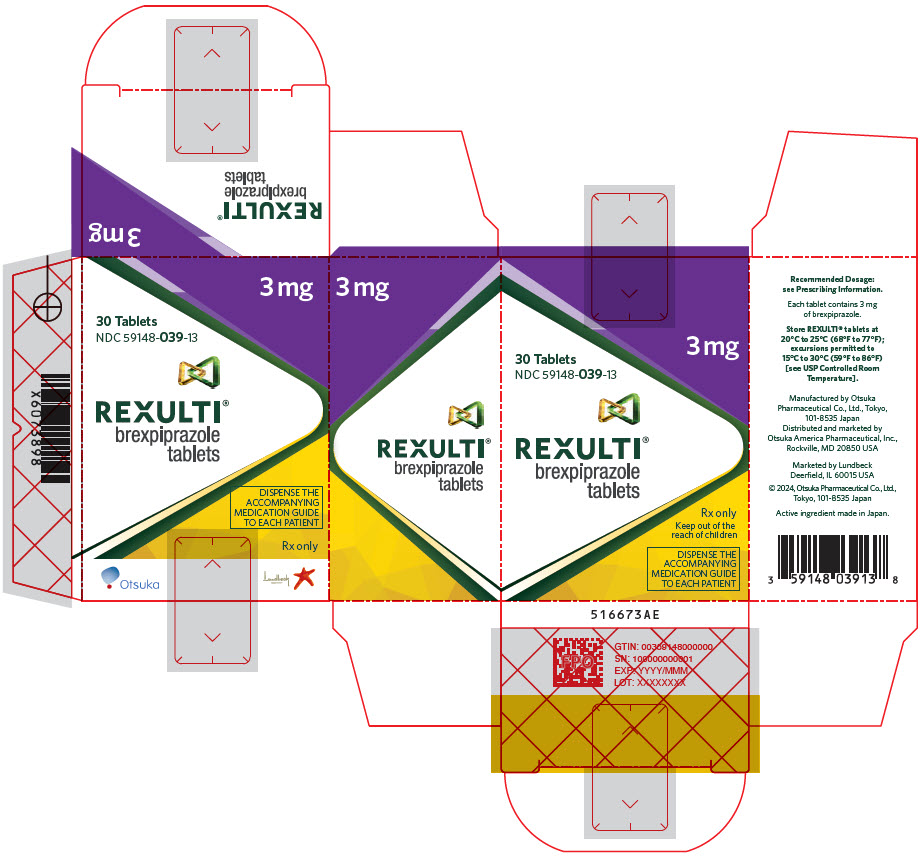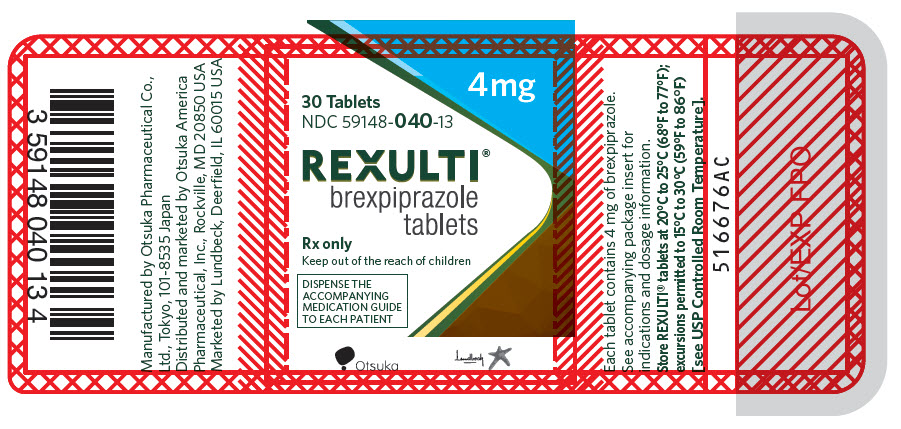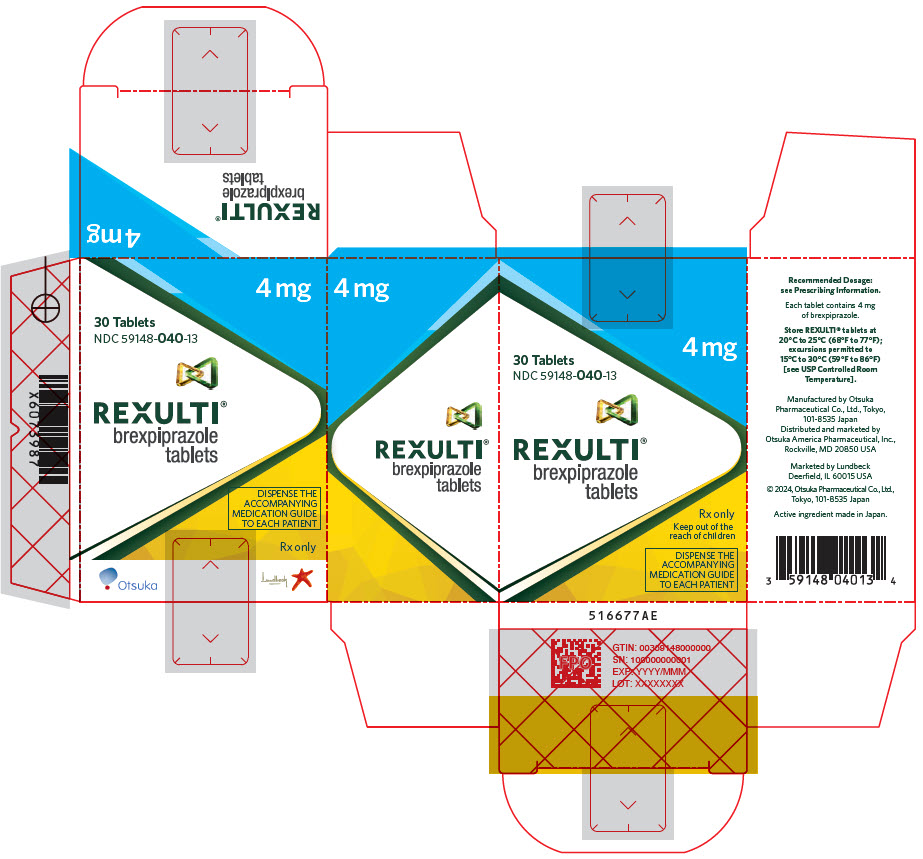 DRUG LABEL: Rexulti
NDC: 59148-035 | Form: TABLET
Manufacturer: Otsuka America Pharmaceutical, Inc.
Category: prescription | Type: HUMAN PRESCRIPTION DRUG LABEL
Date: 20250618

ACTIVE INGREDIENTS: brexpiprazole 0.25 mg/1 1
INACTIVE INGREDIENTS: LACTOSE MONOHYDRATE; STARCH, CORN; MICROCRYSTALLINE CELLULOSE; HYDROXYPROPYL CELLULOSE (1600000 WAMW); LOW-SUBSTITUTED HYDROXYPROPYL CELLULOSE, UNSPECIFIED; MAGNESIUM STEARATE; HYPROMELLOSE, UNSPECIFIED; TALC; TITANIUM DIOXIDE; FERRIC OXIDE RED; FERRIC OXIDE YELLOW; FERROSOFERRIC OXIDE

HIGHLIGHTS OF PRESCRIBING INFORMATION

These highlights do not include all the information needed to use REXULTI safely and effectively. See full prescribing information for REXULTI.
REXULTI® (brexpiprazole) tablets, for oral use
Initial U.S. Approval: 2015

WARNING: INCREASED MORTALITY IN ELDERLY PATIENTS WITH DEMENTIA-RELATED PSYCHOSIS and SUICIDAL THOUGHTS AND BEHAVIORS

See full prescribing information for complete boxed warning.

- Elderly patients with dementia-related psychosis treated with antipsychotic drugs are at increased risk of death. REXULTI is not approved for the treatment of patients with dementia-related psychosis without agitation associated with dementia due to Alzheimer's disease. (5.1)
- Antidepressants increased the risk of suicidal thoughts and behaviors in pediatric and young adult patients. Closely monitor all antidepressant-treated patients for clinical worsening and emergence of suicidal thoughts and behaviors. Safety and effectiveness of REXULTI have not been established in pediatric patients with MDD. (5.2, 8.4)

RECENT MAJOR CHANGES

Warnings and Precautions (5.6) | 5/2025

1 INDICATIONS AND USAGE

REXULTI is an atypical antipsychotic indicated for:

- Use as an adjunctive therapy to antidepressants for the treatment of major depressive disorder (MDD) in adults (1, 14.1)
- Treatment of schizophrenia in adults and pediatric patients ages 13 years and older (1, 14.2)
- Treatment of agitation associated with dementia due to Alzheimer's disease (1, 14.3)

Limitations of Use: REXULTI is not indicated as an as needed ("prn") treatment for agitation associated with dementia due to Alzheimer's disease (1)

2 DOSAGE AND ADMINISTRATION

Administer REXULTI orally once daily with or without food. (2, 12.3)

Indication | Starting Dosage | Recommended Target Dosage | Maximum Dosage
MDD Adults (2.2) | 0.5 mg/day or 1 mg/day | 2 mg/day | 3 mg/day
Schizophrenia Adults (2.3) | 1 mg/day | 2 to 4 mg/day | 4 mg/day
Schizophrenia Pediatric (13 - 17 years) (2.3) | 0.5 mg/day | 2 to 4 mg/day | 4 mg/day
Agitation associated with dementia due to Alzheimer's disease (2.4) | 0.5 mg/day | 2 mg/day | 3 mg/day

- Moderate to Severe Hepatic Impairment: Maximum recommended dosage is 2 mg once daily for patients with MDD or agitation associated with dementia due to Alzheimer's disease and 3 mg once daily for patients with schizophrenia. (2.5)
- CrCl<60 mL/minute: Maximum recommended dosage is 2 mg once daily for patients with MDD or agitation associated with dementia due to Alzheimer's disease and 3 mg once daily for patients with schizophrenia. (2.6)
- See Full Prescribing Information for dosage modifications for CYP2D6 poor metabolizers and for concomitant use with CYP inhibitors or inducers. (2.7)

3 DOSAGE FORMS AND STRENGTHS

Tablets: 0.25 mg, 0.5 mg, 1 mg, 2 mg, 3 mg, and 4 mg (3)

4 CONTRAINDICATIONS

Known hypersensitivity to REXULTI or any of its components (4)

5 WARNINGS AND PRECAUTIONS

- Cerebrovascular Adverse Reactions in Elderly Patients with Dementia-Related Psychosis: Increased incidence of cerebrovascular adverse reactions (e.g., stroke, transient ischemic attack) (5.3)
- Neuroleptic Malignant Syndrome: Manage with immediate discontinuation and close monitoring. (5.4)
- Tardive Dyskinesia: Discontinue if clinically appropriate. (5.5)
- Metabolic Changes: Monitor for hyperglycemia/diabetes mellitus, dyslipidemia, and weight gain. (5.6)
- Pathological Gambling and Other Compulsive Behaviors: Consider dose reduction or discontinuation. (5.7)
- Leukopenia, Neutropenia, and Agranulocytosis: Perform complete blood counts (CBC) in patients with pre-existing low white blood cell count (WBC) or history of leukopenia or neutropenia. Consider discontinuing REXULTI if a clinically significant decline in WBC occurs in absence of other causative factors. (5.8)
- Orthostatic Hypotension and Syncope: Monitor heart rate and blood pressure and warn patients with known cardiovascular or cerebrovascular disease, and risk of dehydration or syncope. (5.9)
- Seizures: Use cautiously in patients with a history of seizures or with conditions that lower the seizure threshold. (5.11)
- Potential for Cognitive and Motor Impairment: Use caution when operating machinery. (5.14)

6 ADVERSE REACTIONS

Most common adverse reactions in adults were (6.1):

- Adult patients with major depressive disorder (adjunctive treatment to antidepressant therapy):: Weight increased, somnolence, and akathisia (≥5% and at least twice the rate for placebo)
- Adult Patients with schizophrenia: Weight increased (≥4% and at least twice the rate for placebo)
- Pediatric patients (13 to 17 years) with schizophrenia: Extrapyramidal symptoms, excluding akathisia (≥5% and at least twice the rate for placebo)
- Adult patients with agitation associated with dementia due to Alzheimer's disease: Nasopharyngitis, dizziness (≥4% and at least twice the rate for placebo)

To report SUSPECTED ADVERSE REACTIONS, contact Otsuka America Pharmaceutical, Inc. at 1-800-438-9927 or FDA at 1-800-FDA-1088 or www.fda.gov/medwatch.

7 DRUG INTERACTIONS

Factors | Dosage Adjustments for REXULTI (2.7)
Strong CYP2D6 [REXULTI may be administered without dosage adjustment in patients with MDD when administered with strong CYP2D6 inhibitors (e.g., paroxetine, fluoxetine).] or CYP3A4 inhibitors | Administer half of recommended dosage.
Strong/moderate CYP2D6 with Strong/moderate CYP3A4 inhibitors | Administer a quarter of the recommended dosage.
Known CYP2D6 poor metabolizers taking strong/moderate CYP3A4 inhibitors | Administer a quarter of the recommended dosage.
Strong CYP3A4 inducers | Double the recommended dosage and further adjust based on clinical response.

8 USE IN SPECIFIC POPULATIONS

Pregnancy: May cause extrapyramidal and/or withdrawal symptoms in neonates with third trimester exposure (8.1)

FULL PRESCRIBING INFORMATION

WARNING: INCREASED MORTALITY IN ELDERLY PATIENTS WITH DEMENTIA-RELATED PSYCHOSIS and SUICIDAL THOUGHTS AND BEHAVIORS

Increased Mortality in Elderly Patients with Dementia-Related Psychosis

Elderly patients with dementia-related psychosis treated with antipsychotic drugs are at an increased risk of death. REXULTI is not approved for the treatment of patients with dementia-related psychosis without agitation associated with dementia due to Alzheimer's disease [see Warnings and Precautions (5.1)].

Suicidal Thoughts and Behaviors

Antidepressants increased the risk of suicidal thoughts and behaviors in pediatric patients and young adult patients in short-term studies. Closely monitor all antidepressant-treated patients for clinical worsening, and for emergence of suicidal thoughts and behaviors [see Warnings and Precautions (5.2)]. The safety and effectiveness of REXULTI have not been established in pediatric patients with MDD [see Warnings and Precautions (5.2), Use in Specific Populations (8.4)].

1 INDICATIONS AND USAGE

REXULTI is indicated for:

- Adjunctive treatment to antidepressants for major depressive disorder (MDD) in adults
- Treatment of schizophrenia in adults and pediatric patients ages 13 years and older
- Treatment of agitation associated with dementia due to Alzheimer's disease

Limitations of Use:

REXULTI is not indicated as an as needed ("prn") treatment for agitation associated with dementia due to Alzheimer's disease [see Clinical Studies (14.3)].

2 DOSAGE AND ADMINISTRATION

2.1 Administration Information

Administer REXULTI orally, once daily with or without food [see Clinical Pharmacology (12.3)]

2.2 Recommended Dosage for Adjunctive Treatment of Major Depressive Disorder (Adults)

The recommended starting REXULTI dosage for the adjunctive treatment of MDD in adults is 0.5 mg or 1 mg orally once daily. Titrate to 1 mg once daily, then titrate to the target dosage of 2 mg once daily (based on the patient's clinical response and tolerability, increase the dosage at weekly intervals). The maximum recommended daily dosage is 3 mg. Periodically reassess to determine the continued need and appropriate dosage for treatment.

2.3 Recommended Dosage for Schizophrenia (Adults and Pediatric Patients 13 to 17 Years)

Adults

The recommended starting REXULTI dosage for the treatment of schizophrenia in adults is 1 mg orally once daily on Days 1 to 4. Titrate to 2 mg once daily on Day 5 through Day 7. On Day 8, the dosage can be increased to the maximum recommended daily dosage of 4 mg based on clinical response and tolerability. The recommended target dosage is 2 mg to 4 mg once daily.

Pediatric Patients (13 to 17 years of age)

The recommended starting REXULTI dosage for the treatment of schizophrenia in pediatric patients 13 to 17 years of age is 0.5 mg orally once daily on Days 1 to 4. On Days 5 through 7, titrate to 1 mg per day and on Day 8 titrate to 2 mg based on clinical response and tolerability. Weekly dose increases can be made in 1 mg increments. A recommended target dosage is 2 to 4 mg once daily. The maximum recommended daily dosage is 4 mg.

2.4 Recommended Dosage for Agitation Associated with Dementia Due to Alzheimer's Disease

The recommended starting REXULTI dosage for the treatment of agitation associated with dementia due to Alzheimer's disease is 0.5 mg orally once daily on Days 1 to 7. Increase the dosage on Days 8 through 14 to 1 mg once daily, and on Day 15 to 2 mg once daily. The recommended target dose is 2 mg once daily. The dosage can be increased to the maximum recommended daily dosage of 3 mg once daily after at least 14 days, based on clinical response and tolerability.

2.5 Recommended Dosage in Patients with Hepatic Impairment

The maximum recommended dosage in patients with moderate to severe hepatic impairment (Child-Pugh score ≥7) is [see Use in Specific Populations (8.7), Clinical Pharmacology (12.3)].

2 mg orally once daily in patients with MDD or agitation associated with dementia due to Alzheimer's disease, and

3 mg orally once daily in patients with schizophrenia

2.6 Recommended Dosage in Patients with Renal Impairment

The maximum recommended dosage in patients with creatinine clearance CrCl<60 mL/minute is [see Use in Specific Populations (8.8), Clinical Pharmacology (12.3)].

2 mg orally once daily in patients with MDD or agitation associated with dementia due to Alzheimer's disease and

3 mg orally once daily in patients with schizophrenia

2.7 Dosage Modifications for CYP2D6 Poor Metabolizers and for Concomitant Use with CYP Inhibitors or Inducers

Dosage modifications are recommended in patients who are known cytochrome P450 (CYP) 2D6 poor metabolizers and in patients taking concomitant CYP3A4 inhibitors, CYP2D6 inhibitors, or strong CYP3A4 inducers (see Table 1). If the concomitant drug is discontinued, adjust the REXULTI dosage to its original level. If the concomitant CYP3A4 inducer is discontinued, reduce the REXULTI dosage to the original level over 1 to 2 weeks [see Drug Interactions (7.1), Clinical Pharmacology (12.3)].

Table 1 Dosage Modifications of REXULTI for CYP2D6 Poor Metabolizers and for Concomitant Use with CYP3A4 Inhibitors, CYP2D6 Inhibitors, or CYP3A4 Inducers
Factors | Adjusted REXULTI Dosage
CYP2D6 Poor Metabolizers
CYP2D6 poor metabolizers | Administer half of the recommended dosage.
Known CYP2D6 poor metabolizers taking strong/moderate CYP3A4 inhibitors | Administer a quarter of the recommended dosage.
Patients Taking CYP2D6 Inhibitors and/or CYP3A4 Inhibitors
Strong CYP2D6 inhibitors [In the clinical studies examining the use of REXULTI for the adjunctive treatment of MDD, dosage was not adjusted for strong CYP2D6 inhibitors (e.g., paroxetine, fluoxetine). Thus, CYP considerations are already factored into general dosing recommendations, and REXULTI may be administered without dosage adjustment in patients with MDD.] | Administer half of the recommended dosage.
Strong CYP3A4 inhibitors | Administer half of the recommended dosage.
Strong/moderate CYP2D6 inhibitors with strong/moderate CYP3A4 inhibitors | Administer a quarter of the recommended dosage.
Patients Taking CYP3A4 Inducers
Strong CYP3A4 inducers | Double the recommended dosage over 1 to 2 weeks.

3 DOSAGE FORMS AND STRENGTHS

REXULTI tablets are available in 6 strengths:

- 0.25 mg tablets are light brown, round, shallow convex, bevel-edged body with "BRX" and "0.25" imprinted on one side.
- 0.5 mg tablets: are light orange, round, shallow convex, bevel-edged body with "BRX" and "0.5" imprinted on one side.
- 1 mg tablets are light yellow, round, shallow convex, bevel-edged body with "BRX" and "1" imprinted on one side.
- 2 mg tablets are light green, round, shallow convex, bevel-edged body with "BRX" and "2" imprinted on one side.
- 3 mg tablets are light purple, round, shallow convex, bevel-edged body with "BRX" and "3" imprinted on one side.
- 4 mg tablets are white, round, shallow convex, bevel-edged body with "BRX" and "4" imprinted on one side.

4 CONTRAINDICATIONS

REXULTI is contraindicated in patients with a known hypersensitivity to brexpiprazole or any of its components. Reactions have included rash, facial swelling, urticaria, and anaphylaxis.

5 WARNINGS AND PRECAUTIONS

5.1 Increased Mortality in Elderly Patients with Dementia-Related Psychosis

Elderly patients with dementia-related psychosis treated with antipsychotic drugs are at an increased risk of death. Analyses of 17 placebo-controlled trials (modal duration of 10 weeks), largely in patients taking atypical antipsychotic drugs, revealed a risk of death in drug-treated patients of between 1.6 to 1.7 times the risk of death in placebo-treated patients. Over the course of a typical 10-week controlled trial, the rate of death in the drug-treated patients was about 4.5%, compared to a rate of about 2.6% in the placebo group.

Although the causes of death were varied, most of the deaths appeared to be either cardiovascular (e.g., heart failure, sudden death) or infectious (e.g., pneumonia) in nature. REXULTI is not approved for the treatment of patients with dementia-related psychosis without agitation associated with dementia due to Alzheimer's disease [see Boxed Warning, Warnings and Precautions (5.3)].

5.2 Suicidal Thoughts and Behaviors in Children, Adolescents, and Young Adults

In pooled analyses of placebo-controlled trials of antidepressant drugs (SSRIs and other antidepressant classes) that included approximately 77,000 adult patients and over 4,400 pediatric patients, the incidence of suicidal thoughts and behaviors in patients 24 years of age and younger was greater in antidepressant-treated patients than in placebo-treated patients. The drug-placebo differences in the number of cases of suicidal thoughts and behaviors per 1,000 patients treated are provided in Table 2.

No suicides occurred in any of the pediatric studies. There were suicides in the adult studies, but the number was not sufficient to reach any conclusion about antidepressant drug effect on suicide.

Table 2 Risk Differences of the Number of Patients with Suicidal Thoughts or Behaviors in the Pooled Placebo-Controlled Trials of Antidepressants in Pediatric [REXULTI is not approved in pediatric patients with MDD.] and Adult Patients
Age Range (years) | Drug-Placebo Difference in Number of Patients with Suicidal Thoughts or Behaviors per 1,000 Patients Treated
 | Increases Compared to Placebo
<18 | 14 additional patients
18 to 24 | 5 additional patients
 | Decreases Compared to Placebo
25 to 64 | 1 fewer patient
≥65 | 6 fewer patients

It is unknown whether the risk of suicidal thoughts and behaviors in children, adolescents, and young adults extends to longer-term use, i.e., beyond four months. However, there is substantial evidence from placebo-controlled maintenance studies in adults with MDD that antidepressants delay the recurrence of depression.

Monitor all antidepressant-treated patients for clinical worsening and emergence of suicidal thoughts and behaviors, especially during the initial few months of drug therapy and at times of dosage changes. Counsel family members or caregivers of patients to monitor for changes in behavior and to alert the healthcare provider. Consider changing the therapeutic regimen, including possibly discontinuing REXULTI, in patients whose depression is persistently worse or who are experiencing emergent suicidal thoughts or behaviors.

5.3 Cerebrovascular Adverse Reactions Including Stroke in Elderly Patients with Dementia-Related Psychosis

In placebo-controlled trials in elderly patients with dementia, patients randomized to risperidone, aripiprazole, and olanzapine had a higher incidence of stroke and transient ischemic attack, including fatal stroke. REXULTI is not approved for the treatment of patients with dementia-related psychosis without agitation associated with dementia due to Alzheimer's disease [see Boxed Warning, Warnings and Precautions (5.1)].

5.4 Neuroleptic Malignant Syndrome (NMS)

Neuroleptic Malignant Syndrome (NMS), a potentially fatal symptom complex, has been reported in association with administration of antipsychotic drugs, including REXULTI.

Clinical manifestations of NMS are hyperpyrexia, muscle rigidity, altered mental status, and evidence of autonomic instability (irregular pulse or blood pressure, tachycardia, diaphoresis and cardiac dysrhythmia). Additional signs may include elevated creatinine phosphokinase, myoglobinuria (rhabdomyolysis), and acute renal failure.

If NMS is suspected, immediately discontinue REXULTI and provide intensive symptomatic treatment and monitoring.

5.5 Tardive Dyskinesia

Tardive dyskinesia, a syndrome consisting of potentially irreversible, involuntary, dyskinetic movements, may develop in patients treated with antipsychotic drugs. The risk appears to be highest among the elderly, especially elderly women, but it is impossible to predict which patients will develop the syndrome. Whether antipsychotic drugs differ in their potential to cause tardive dyskinesia is unknown.

The risk of tardive dyskinesia and the likelihood that it will become irreversible appear to increase as the duration of treatment and the cumulative dose increases. The syndrome can develop after relatively brief treatment periods, at low doses. It may also occur after discontinuation of treatment.

Tardive dyskinesia may remit, partially or completely, if antipsychotic treatment is discontinued. Antipsychotic treatment itself may suppress (or partially suppress) the signs and symptoms of the syndrome, possibly masking the underlying process. The effect that symptomatic suppression has upon the long-term course of tardive dyskinesia is unknown.

Given these considerations, REXULTI should be prescribed in a manner most likely to reduce the occurrence of tardive dyskinesia. Chronic antipsychotic treatment should generally be reserved for patients who suffer from a chronic illness that 1) is known to respond to antipsychotic drugs and 2) for whom alternative, equally effective, but potentially less harmful treatments are not available or appropriate. In patients who do require chronic treatment, use the lowest dose and the shortest duration of treatment needed to produce a satisfactory clinical response. Periodically reassess the need for continued treatment.

If signs and symptoms of tardive dyskinesia appear in a patient treated with REXULTI, drug discontinuation should be considered. However, some patients may require treatment with REXULTI despite the presence of the syndrome.

5.6 Metabolic Changes

Atypical antipsychotic drugs, including REXULTI, have caused metabolic changes including hyperglycemia, diabetes mellitus, dyslipidemia, and body weight gain. Although all of the drugs in the class to date have been shown to produce some metabolic changes, each drug has its own specific risk profile.

Hyperglycemia/Diabetes Mellitus

Hyperglycemia and diabetes mellitus, in some cases extreme and associated with diabetic ketoacidosis hyperosmolar coma or death, have been reported in patients treated with atypical antipsychotics. There have been reports of hyperglycemia in patients treated with REXULTI. Assess fasting plasma glucose before or soon after initiation of antipsychotic medication and monitor periodically during long-term treatment.

Adjunctive Treatment of Major Depressive Disorder

In the 6-week placebo-controlled, fixed-dose clinical studies in adult patients with MDD, the proportions of patients with shifts in fasting glucose from normal (<100 mg/dL) to high (≥126 mg/dL) and borderline (≥100 and <126 mg/dL) to high were similar in patients treated with REXULTI and placebo. In the long-term, open-label depression studies, 5% of adult patients with normal baseline fasting glucose experienced a shift to high while taking REXULTI plus an antidepressant (ADT); 25% of patients with borderline fasting glucose experienced shifts to high. Combined, 9% of patients with normal or borderline fasting glucose experienced shifts to high fasting glucose during the long-term depression studies.

Schizophrenia (Adults)

In the 6-week placebo-controlled, fixed-dose clinical studies in adult patients with schizophrenia, the proportions of patients with shifts in fasting glucose from normal (<100 mg/dL) to high (≥126 mg/dL) or borderline (≥100 and <126 mg/dL) to high were similar in patients treated with REXULTI and placebo. In the long-term, open-label schizophrenia studies, 8% of adult patients with normal baseline fasting glucose experienced a shift from normal to high while taking REXULTI; 17% of patients with borderline fasting glucose experienced shifts from borderline to high. Combined, 10% of patients with normal or borderline fasting glucose experienced shifts to high fasting glucose during the long-term schizophrenia studies.

Schizophrenia Pediatric Patients (13 to 17 years of age)

In a 6-week, placebo-controlled study in pediatric patients with schizophrenia, the proportion of patients with shifts in fasting glucose from normal (<100 mg/dL) to high (≥126 mg/dL) or borderline (≥100 and <126 mg/dL) to high were similar in patients treated with REXULTI and placebo. In this study, 1.1% of pediatric patients with normal baseline fasting glucose experienced a shift from normal (<100 mg/dL) to high (≥126 mg/dL) while taking REXULTI.

In the long-term, open-label study in pediatric patients with schizophrenia, 2.7% of pediatric patients with normal baseline fasting glucose experienced a shift from normal (<100 mg/dL) to high (≥126 mg/dL) while taking REXULTI.

Agitation Associated with Dementia Due to Alzheimer's Disease

In the 12-week placebo-controlled, fixed-dose studies in patients (51 to 90 years of age) with agitation associated with dementia due to Alzheimer's disease, the proportions of patients with shifts in fasting glucose from normal (<100 mg/dL) to high (≥126 mg/dL) or impaired (≥100 and <126 mg/dL) to high were similar in patients treated with REXULTI (14%) and patients treated with placebo (16%).

Of the patients who were previously treated with REXULTI for 12-weeks and continued into a 12-week, active-treatment extension study, 15% of patients with normal baseline fasting glucose experienced a shift from normal (<100 mg/dL) to high (≥126 mg/dL) fasting glucose while taking REXULTI; 30% of patients with impaired fasting glucose experienced shifts from impaired fasting glucose (≥100 and <126 mg/dL) to high fasting glucose. Combined, 20% of patients with normal or impaired fasting glucose experienced shifts to high fasting glucose.

Dyslipidemia

Atypical antipsychotics cause adverse alterations in lipids. Before or soon after initiation of antipsychotic medication, obtain a fasting lipid profile at baseline and monitor periodically during treatment.

Adjunctive Treatment of Major Depressive Disorder

In the 6-week placebo-controlled, fixed-dose clinical studies in adult patients with MDD, changes in fasting total cholesterol, LDL cholesterol, and HDL cholesterol were similar in REXULTI- and placebo-treated patients. Table 3 shows the proportions of patients with changes in fasting triglycerides.

Table 3 Change in Fasting Triglycerides in the 6-Week Placebo-Controlled, Fixed-Dose MDD Studies
Proportion of Patients with Shifts Baseline to Post-Baseline
Triglycerides | Placebo | 1 mg/day | 2 mg/day | 3 mg/day
Normal to High (<150 mg/dL to ≥200 and <500 mg/dL) | 6% (15/257) [denotes n/N where N=the total number of patients who had a measurement at baseline and at least one post-baseline result;n=the number of patients with shift] | 5% (7/145) | 13% (15/115) | 9% (13/150)
Normal/Borderline to Very High (<200 mg/dL to ≥500 mg/dL) | 0% (0/309) | 0% (0/177) | 0.7% (1/143) | 0% (0/179)

In the long-term, open-label depression studies, shifts in baseline fasting cholesterol from normal to high were reported in 9% (total cholesterol), 3% (LDL cholesterol), and shifts in baseline from normal to low were reported in 14% (HDL cholesterol) of patients taking REXULTI. Of patients with normal baseline triglycerides, 17% experienced shifts to high, and 0.2% experienced shifts to very high. Combined, 0.6% of patients with normal or borderline fasting triglycerides experienced shifts to very high fasting triglycerides during the long-term depression studies.

Schizophrenia (Adults)

In the 6-week placebo-controlled, fixed-dose clinical studies in adult patients with schizophrenia, changes in fasting total cholesterol, LDL cholesterol, and HDL cholesterol were similar in REXULTI- and placebo-treated patients. Table 4 shows the proportions of patients with changes in fasting triglycerides.

Table 4 Change in Fasting Triglycerides in the 6-Week Placebo-Controlled, Fixed-Dose Schizophrenia Studies in Adult Patients
Proportion of Patients with Shifts Baseline to Post-Baseline
Triglycerides | Placebo | 1 mg/day | 2 mg/day | 4 mg/day
Normal to High (<150 mg/dL to ≥200 and <500 mg/dL) | 6% (15/253) [denotes n/N where N=the total number of patients who had a measurement at baseline and at least one post-baseline result;n=the number of patients with shift] | 10% (7/72) | 8% (19/232) | 10% (22/226)
Normal/Borderline to Very High (<200 mg/dL to ≥500 mg/dL) | 0% (0/303) | 0% (0/94) | 0% (0/283) | 0.4% (1/283)

In the long-term, open-label schizophrenia studies in adult patients, shifts in baseline fasting cholesterol from normal to high were reported in 6% (total cholesterol), 2% (LDL cholesterol), and shifts in baseline from normal to low were reported in 17% (HDL cholesterol) of patients taking REXULTI. Of patients with normal baseline triglycerides, 13% experienced shifts to high, and 0.4% experienced shifts to very high triglycerides. Combined, 0.6% of patients with normal or borderline fasting triglycerides experienced shifts to very high fasting triglycerides during the long-term schizophrenia studies.

Schizophrenia [Pediatric Patients (13 to 17 years of age)]

The safety and efficacy of REXULTI have not been established in patients under the age of 13 years. In a 6-week, placebo-controlled study in pediatric patients with schizophrenia, no clinically meaningful changes in fasting cholesterol, LDL cholesterol, HDL cholesterol, and triglycerides were observed between the REXULTI and placebo groups.

In the long-term, open-label study in pediatric patients with schizophrenia, shifts in baseline fasting total cholesterol from normal to high (<170 to ≥200 mg/dL) were reported in 7% of patients taking REXULTI, and shifts in baseline HDL cholesterol from normal to low (>45 to <40 mg/dL) were reported in 10%% of patients taking REXULTI. Of patients with normal baseline triglycerides, 15% experienced shifts from normal to high (<90 to ≥130 mg/dL).

Agitation Associated with Dementia Due to Alzheimer's Disease

In the 12-week placebo-controlled, fixed-dose clinical studies in patients (55 to 90 years of age) with agitation associated with dementia due to Alzheimer's disease, changes in total cholesterol, LDL cholesterol, and HDL cholesterol were similar in REXULTI- and placebo-treated patients.

Table 5 shows the proportions of patients with changes in fasting triglycerides in REXULTI- and placebo-treated patients.

Table 5 Change in Fasting Triglycerides in the 12-Week Placebo-Controlled, Fixed-Dose Agitation Associated with Dementia Due to Alzheimer's Disease Studies
Proportion of Patients with Shifts Baseline to Post-Baseline
Triglycerides | Placebo | 1 mg/day | 2 mg/day | 3 mg/day
Normal to High (<150 and 200 to <500 mg/dL) | 6% (10/157) [denotes n/N where N=the total number of patients who had a measurement at baseline and at least one post-baseline result;n=the number of patients with shift] | 9% (9/99) | 13% (17/133) | 6% (6/94)
Borderline to High (150 and <200mg/dL to 200 and <500 mg/dL) | 12% (3/26) | 33% (2/6) | 28% (7/25) | 26% (6/23)
Normal/Borderline to High (<200 mg/dL to 200 and <500 mg/dL) | 7% (13/183) | 11% (11/105) | 15% (24/158) | 10% (12/117)

Of the patients who were previously treated with REXULTI for 12 weeks and continued into a 12-week, active-treatment extension study, 9% of patients taking REXULTI showed shifts in baseline fasting total cholesterol from normal (<200 mg/dL) to high (≥240 mg/dL), and 16% of patients taking REXULTI showed shifts in baseline HDL cholesterol from normal to low (≥40 to <40 mg/dL). Of the patients with normal baseline triglycerides, 18% experienced shifts from normal (<150 mg/dL) to high (200 to <500 mg/dL).

Weight Gain

Weight gain has been observed in patients treated with atypical antipsychotics, including REXULTI. Monitor weight at baseline and frequently thereafter.

Adjunctive Treatment of Major Depressive Disorder: Table 6 shows weight gain data at last visit and percentage of adult patients with ≥7% increase in body weight at endpoint from the 6-week placebo-controlled, fixed-dose clinical studies in patients with MDD.

Table 6 Increases in Body Weight in the 6-Week Placebo-Controlled, Fixed-Dose MDD Studies
 | Placebo | 1 mg/day | 2 mg/day | 3 mg/day
 | n=407 | n=225 | n=187 | n=228
Mean Change from Baseline (kg) at Last Visit
All Patients | +0.3 | +1.3 | +1.6 | +1.6
Proportion of Patients with a ≥7% Increase in Body Weight (kg) at Any Visit (n/N [N=the total number of patients who had a measurement at baseline and at least one post-baseline result;n=the number of patients with a shift ≥7%])
 | 2% | 5% | 5% | 2%
 | (8/407) | (11/225) | (9/187) | (5/228)

In the long-term, open-label depression studies, 4% of patients discontinued due to weight increase. REXULTI was associated with mean change from baseline in weight of 2.9 kg at Week 26 and 3.1 kg at Week 52. In the long-term, open-label depression studies, 30% of patients demonstrated a ≥7% increase in body weight, and 4% demonstrated a ≥7% decrease in body weight.

Schizophrenia (Adults)

Table 7 shows weight gain data at last visit and percentage of adult patients with ≥7% increase in body weight at endpoint from the 6-week placebo-controlled, fixed-dose clinical studies in adult patients with schizophrenia.

Table 7 Increases in Body Weight in the 6-Week Placebo-Controlled, Fixed-Dose Schizophrenia Studies in Adult Patients
 | Placebo | 1 mg/day | 2 mg/day | 4 mg/day
 | n=362 | n=120 | n=362 | n=362
Mean Change from Baseline (kg) at Last Visit
All Patients | +0.2 | +1.0 | +1.2 | +1.2
Proportion of Patients with a ≥7% Increase in Body Weight (kg) at Any Visit ([denotes n/N where N=the total number of patients who had a measurement at baseline and at least one post-baseline result;n=the number of patients with a shift ≥7%] n/N)
 | 4% | 10% | 11% | 10%
 | (15/362) | (12/120) | (38/362) | (37/362)

In the long-term, open-label schizophrenia studies in adult patients, 0.6% of patients discontinued due to weight increase. REXULTI was associated with mean change from baseline in weight of 1.3 kg at Week 26 and 2.0 kg at Week 52. In the long-term, open label schizophrenia studies, 20% of patients demonstrated a ≥7% increase in body weight, and 10% demonstrated a ≥7% decrease in body weight.

Schizophrenia [Pediatric Patients (13 to 17 years of age)]

In a 6-week, placebo-controlled study in pediatric patients with schizophrenia, no patients discontinued due to weight increase. The mean increase in weight from baseline to last visit was 0.8 kg in the REXULTI group and no changes were seen in the placebo groups. The percentage of pediatric patients demonstrating a ≥7% increase in body weight was 8.2% in the REXULTI group and 4.9% in the placebo group.

In the long-term, open label study in pediatric patients with schizophrenia, 0.5% of patients discontinued due to weight increase. The mean increase in weight from the open-label study baseline to last visit was 3.8 kg. To adjust for normal growth, z-scores were derived (measured in standard deviations [SD]), which normalize for natural growth of children and adolescents by comparisons to age- and gender- matched population standards. A z-score change <0.5 SD is considered not clinically significant. In this study, the mean change in z-score from open-label baseline to last visit was 0.10 SD for body weight, while 20% of patients had an increase in age-and-gender-adjusted body weight z-score of at least 0.5 SD from baseline. When treating pediatric, weight gain should be monitored and assessed against that expected for normal growth.

Agitation Associated with Dementia Due to Alzheimer's Disease

In the 12-week placebo-controlled, fixed-dose clinical studies in patients (51 to 90 years of age) with agitation associated with dementia due to Alzheimer's disease, the proportion of the patients with a ≥7% increase in body weight (kg) at any visit were 2% in REXULTI compared to 0% in placebo group.

In patients who were previously treated with REXULTI for 12 weeks and who continued into a 12-week, active-treatment extension study, there was no mean change in weight (kg) from baseline to last visit in association with REXULTI. In this extension study, 4% of patients demonstrated ≥7% increase in body weight, and 5% demonstrated a ≥7% decrease in body weight from baseline to last visit.

5.7 Pathological Gambling and Other Compulsive Behaviors

Post-marketing case reports suggest that patients can experience intense urges, particularly for gambling, and the inability to control these urges while taking REXULTI. Other compulsive urges, reported less frequently, include sexual urges, shopping, eating, or binge eating, and other impulsive or compulsive behaviors. Because patients may not recognize these behaviors as abnormal, it is important for prescribers to ask patients or their caregivers specifically about the development of new or intense gambling urges, compulsive sexual urges, compulsive shopping, binge or compulsive eating, or other urges while being treated with REXULTI. In some cases, although not all, urges were reported to have stopped when the dose was reduced, or the medication was discontinued. Compulsive behaviors may result in harm to the patient and others if not recognized. Consider dose reduction or stopping the medication if a patient develops such urges.

5.8 Leukopenia, Neutropenia, and Agranulocytosis

Leukopenia and neutropenia have been reported during treatment with antipsychotic agents. Agranulocytosis (including fatal cases) has been reported with other agents in this class.

Possible risk factors for leukopenia and neutropenia include pre-existing low white blood cell count (WBC) or absolute neutrophil count (ANC) and history of drug-induced leukopenia or neutropenia. In patients with a pre-existing low WBC or ANC or a history of drug-induced leukopenia or neutropenia, perform a complete blood count (CBC) frequently during the first few months of therapy. In such patients, consider discontinuation of REXULTI at the first sign of a clinically significant decline in WBC in the absence of other causative factors.

Monitor patients with clinically significant neutropenia for fever or other symptoms or signs of infection and treat promptly if such symptoms or signs occur. Discontinue REXULTI in patients with absolute neutrophil count <1000/mm^3 and follow their WBC until recovery.

5.9 Orthostatic Hypotension and Syncope

Atypical antipsychotics cause orthostatic hypotension and syncope. Generally, the risk is greatest during initial dose titration and when increasing the dose. In the short-term, placebo-controlled clinical studies of REXULTI plus ADT in adult patients with MDD, the incidence of orthostatic hypotension-related adverse reactions in REXULTI plus ADT-treated patients compared to placebo plus ADT-treated patients included: dizziness (2% versus 2%) and orthostatic hypotension (0.1% versus 0%). In the short-term, placebo-controlled clinical studies of REXULTI in adult patients with schizophrenia, the incidence of orthostatic hypotension-related adverse reactions in REXULTI-treated patients compared to placebo patients included: dizziness (2% versus 2%), orthostatic hypotension (0.4% versus 0.2%), and syncope (0.1% versus 0%). In 12-week, placebo-controlled clinical studies of REXULTI in patients with agitation associated with dementia due to Alzheimer's disease, the incidence of orthostatic hypotension-related adverse reactions in patients treated with REXULTI compared to patients treated with placebo included: dizziness (3% versus 3%), orthostatic hypotension (1% versus 1%), and syncope (0.2% versus 0.8%).

Orthostatic vital signs should be monitored in patients who are vulnerable to hypotension (e.g., elderly patients, patients with dehydration, hypovolemia, concomitant treatment with antihypertensive medication), patients with known cardiovascular disease (history of myocardial infarction, ischemic heart disease, heart failure, or conduction abnormalities), and patients with cerebrovascular disease. REXULTI has not been evaluated in patients with a recent history of myocardial infarction or unstable cardiovascular disease. Such patients were excluded from the premarketing clinical studies.

5.10 Falls

Antipsychotics, including REXULTI, may cause somnolence, postural hypotension, motor, and sensory instability, which may lead to falls and, consequently, fractures or other injuries. For patients with diseases, conditions, or medications that could exacerbate these effects, complete fall risk assessments when initiating antipsychotic treatment and recurrently for patients on long-term antipsychotic treatment.

5.11 Seizures

Like other antipsychotic drugs, REXULTI may cause seizures. This risk is greatest in patients with a history of seizures or with conditions that lower the seizure threshold. Conditions that lower the seizure threshold may be more prevalent in older patients.

5.12 Body Temperature Dysregulation

Atypical antipsychotics may disrupt the body's ability to reduce core body temperature. Strenuous exercise, exposure to extreme heat, dehydration, and anticholinergic medications may contribute to an elevation in core body temperature; use REXULTI with caution in patients who may experience these conditions.

5.13 Dysphagia

Esophageal dysmotility and aspiration have been associated with antipsychotic drug use. Antipsychotic drugs, including REXULTI, should be used cautiously in patients at risk for aspiration.

5.14 Potential for Cognitive and Motor Impairment

REXULTI, like other antipsychotics, may cause somnolence and has the potential to impair judgment, thinking, or motor skills. In the 6-week placebo-controlled clinical studies in patients with MDD, somnolence (including sedation and hypersomnia) was reported in 4% of REXULTI plus ADT-treated patients compared to 1% of placebo plus ADT-treated patients.

In the 6-week placebo-controlled clinical studies in adult patients with schizophrenia, somnolence (including sedation and hypersomnia) was reported in 5% of REXULTI-treated patients compared to 3% of placebo-treated patients.

In the 12-week placebo-controlled, fixed-dose clinical studies in patients (51 to 90 years of age) with agitation associated with dementia due to Alzheimer's disease, somnolence (including sedation) was reported in 3% of patients treated with REXULTI compared to 1% of patients treated with placebo.

Patients should be cautioned about operating hazardous machinery, including motor vehicles, until they are reasonably certain that REXULTI therapy does not affect them adversely.

6 ADVERSE REACTIONS

The following adverse reactions are discussed in more detail in other sections of the labeling:

- Increased Mortality in Elderly Patients with Dementia-Related Psychosis [see Boxed Warning, Warnings and Precautions (5.1)]
- Suicidal Thoughts and Behaviors in Adolescents and Young Adults [see Boxed Warning, Warnings and Precautions (5.2)]
- Cerebrovascular Adverse Reactions Including Stroke in Elderly Patients with Dementia-Related Psychosis [see Warnings and Precautions (5.3)]
- Neuroleptic Malignant Syndrome (NMS) [see Warnings and Precautions (5.4)]
- Tardive Dyskinesia [see Warnings and Precautions (5.5)]
- Metabolic Changes [see Warnings and Precautions (5.6)]
- Pathological Gambling and Other Compulsive Behaviors [see Warnings and Precautions (5.7)]
- Leukopenia, Neutropenia, and Agranulocytosis [see Warnings and Precautions (5.8)]
- Orthostatic Hypotension and Syncope [see Warnings and Precautions (5.9)]
- Falls [see Warnings and Precautions (5.10)]
- Seizures [see Warnings and Precautions (5.11)]
- Body Temperature Dysregulation [see Warnings and Precautions (5.12)]
- Dysphagia [see Warnings and Precautions (5.13)]
- Potential for Cognitive and Motor Impairment [see Warnings and Precautions (5.14)]

6.1 Clinical Trials Experience

Because clinical trials are conducted under widely varying conditions, adverse reaction rates observed in the clinical trials of a drug cannot be directly compared to rates in the clinical trials of another drug and may not reflect the rates observed in clinical practice.

The most common adverse reactions in adult patients in clinical trials (≥5%) were weight increased, akathisia, headache, somnolence, and insomnia.

The most common adverse reactions in pediatric patients in clinical trials (≥5%) were weight increased, somnolence, headache, akathisia, and nasopharyngitis.

Brexpiprazole has been evaluated for safety in 12,550 adult patients who participated in multiple-dose clinical trials for major depressive disorder, schizophrenia, agitation associated with dementia due to Alzheimer's disease, attention deficit hyperactivity disorder (ADHD), post-traumatic stress disorder (PTSD), bipolar mania, and borderline personality disorder (BPD). Among them, 3,870 patients were treated with brexpiprazole for at least 180 days, and 1,910 patients were treated for at least one year of exposure.

Additionally, brexpiprazole has been evaluated for safety in 119 pediatric patients who participated in short-term trials, and 314 patients in long-term multiple-dose clinical trials for pediatric schizophrenia and autism spectrum disorders (ASD).

Adjunctive Treatment in Major Depressive Disorder (MDD)

The safety of REXULTI was evaluated in 1054 adult patients (18 to 65 years of age) diagnosed with MDD who participated in two 6-week placebo-controlled, fixed-dose clinical studies in patients with major depressive disorder in which REXULTI was administered at doses of 1 mg to 3 mg daily as adjunctive treatment to continued antidepressant therapy; patients in the placebo group continued to receive antidepressant therapy [see Clinical Studies (14.1)].

Adverse Reactions Reported as Reasons for Discontinuation of Treatment

A total of 3% (17/643) of REXULTI-treated patients and 1% (3/411) of placebo-treated patients discontinued due to adverse reactions.

Adverse Reactions in REXULTI Studies for Adjunctive MDD in Adults

Adverse reactions associated with the adjunctive use of REXULTI (incidence of 2% or greater and adjunctive REXULTI incidence greater than adjunctive placebo) that occurred during acute therapy (up to 6-weeks in patients with MDD) are shown in Table 8.

Table 8 Adverse Reactions in ≥2% of REXULTI-Treated Patients and Greater than Placebo in Pooled 6-Week Placebo-Controlled, Fixed-Dose Adjunctive MDD Studies in Adults (Study 1 and Study 2)
 | Placebo (N=411) % | REXULTI
 | Placebo (N=411) % | 1 mg/day (N=226) % | 2 mg/day (N=188) % | 3 mg/day (N=229) % | All REXULTI (N=643) %
Gastrointestinal Disorders
Constipation | 1 | 3 | 2 | 1 | 2
General Disorders and Administration Site Conditions
Fatigue | 2 | 3 | 2 | 5 | 3
Infections and Infestations
Nasopharyngitis | 2 | 7 | 1 | 3 | 4
Investigations
Weight Increased | 2 | 7 | 8 | 6 | 7
Blood Cortisol Decreased | 1 | 4 | 0 | 3 | 2
Metabolism and Nutrition
Increased Appetite | 2 | 3 | 3 | 2 | 3
Nervous System Disorders
Akathisia | 2 | 4 | 7 | 14 | 9
Headache | 6 | 9 | 4 | 6 | 7
Somnolence | 0.5 | 4 | 4 | 6 | 5
Tremor | 2 | 4 | 2 | 5 | 4
Dizziness | 1 | 1 | 5 | 2 | 3
Psychiatric Disorders
Anxiety | 1 | 2 | 4 | 4 | 3
Restlessness | 0 | 2 | 3 | 4 | 3

Dose-Related Adverse Reactions in the Adjunctive MDD Studies

In Studies 1 and 2, among the adverse reactions that occurred at ≥2% incidence in the patients treated with REXULTI plus ADT, the incidences of akathisia and restlessness increased with increases in dose.

Schizophrenia

Adults

The safety of REXULTI was evaluated in 852 adult patients (18 to 65 years of age) diagnosed with schizophrenia who participated in two 6-week placebo-controlled, fixed-dose clinical studies in which REXULTI was administered at daily doses of 1 mg, 2 mg, and 4 mg [see Clinical Studies (14.2)].

Adverse Reactions Occurring at an Incidence of 2% or More in Patients Treated with REXULTI for Schizophrenia

Adverse reactions associated with REXULTI (incidence of 2% or greater and REXULTI incidence greater than placebo) during short-term (up to 6 weeks) studies in adult patients with schizophrenia are shown in Table 9.

Table 9 Adverse Reactions in ≥2% of REXULTI-Treated Patients and Greater than Placebo in Pooled 6-Week Placebo-Controlled, Fixed-Dose Schizophrenia Studies in Adult Patients (Study 3 and Study 4)
 | Placebo (N=368) % | REXULTI
 | Placebo (N=368) % | 1 mg/day (N=120) % | 2 mg/day (N=368) % | 4 mg/day (N=364) % | ALL REXULTI (N=852) %
Gastrointestinal Disorders
Dyspepsia | 2 | 6 | 2 | 3 | 3
Diarrhea | 2 | 1 | 3 | 3 | 3
Investigations
Weight Increased | 2 | 3 | 4 | 4 | 4
Blood Creatinine Phosphokinase Increased | 1 | 4 | 2 | 2 | 2
Nervous System Disorders
Akathisia | 5 | 4 | 5 | 7 | 6
Tremor | 1 | 2 | 2 | 3 | 3
Sedation | 1 | 2 | 2 | 3 | 2

Pediatric Patients (13 to 17 years of age)]

The safety of REXULTI was evaluated in 110 pediatric patients (13 to 17 years of age) diagnosed with schizophrenia who participated in a 6-week, placebo-controlled, clinical study in which REXULTI was administered at daily doses of 2 mg to 4 mg [see Clinical Studies (14.2)].

Adverse Reactions Occurring at an Incidence of 2% or More in Pediatric Patients (13 to 17 years of age) Treated with REXULTI for Schizophrenia

Adverse reactions associated with REXULTI (incidence of 2% or greater and REXULTI incidence greater than placebo) during short-term (up to 6 weeks) study in pediatric patients with schizophrenia are shown in Table 10.

Table 10 Adverse Reactions in ≥2% of REXULTI-Treated Patients and Greater than Placebo in 6-Week Placebo- and Active Controlled, Schizophrenia Study in Pediatric Patients 13 to 17 years of age (Study 5)
 | Placebo (N=104) % | REXULTI (N=110) %
Gastrointestinal Disorders
Nausea | 4 | 6
Nervous System Disorders
Akathisia | 3 | 4
Extrapyramidal Symptoms [Extrapyramidal Symptoms includes: blepharospasm, dystonia, extrapyramidal disorder, eye movement disorder, hypokinesia, muscle rigidity, musculoskeletal stiffness, psychomotor hyperactivity, tremor] | 3 | 6
Headache | 5 | 6

Agitation Associated with Dementia Due to Alzheimer's Disease

The safety of REXULTI was evaluated in 503 patients (51 to 90 years of age), with a probable diagnosis of agitation associated with dementia due to Alzheimer's disease, who participated in two 12-week placebo-controlled, fixed-dose clinical studies in which REXULTI was administered at daily doses of 2 mg to 3 mg [see Clinical Studies (14.3)].

Discontinuation of Treatment Due to Adverse Reactions

In two 12-week placebo-controlled, fixed-dose, clinical studies, a total of 5.6% (28/503) of patients treated with REXULTI and 4.8% (12/251) of patients treated with placebo discontinued due to adverse reactions.

Adverse Reactions Occurring at an Incidence of 2% or More in Patients Treated with REXULTI for Agitation Associated with Dementia Due to Alzheimer's Disease

Adverse reactions associated with REXULTI (incidence ≥2% and greater than placebo) during the 12-week fixed-dose clinical studies in geriatric patients for treatment of agitation associated with dementia due to Alzheimer's disease are shown in Table 11.

Table 11 Adverse Reactions in ≥2% of REXULTI-Treated Patients and Greater than Placebo in Pooled 12-Week Placebo-Controlled, Fixed-Dose Agitation Associated with Dementia due to Alzheimer's Disease Studies (Study 6 and Study 7)
 | Placebo (N=251) % | REXULTI
 | Placebo (N=251) % | 1 mg/day [1 mg once day REXULTI dosage is not a recommended dosage for the treatment of agitation associated with dementia due to Alzheimer's disease [see Dosage and Administration (2.4)].] (N=137) % | 2 mg/day (N=213) % | 3 mg/day (N=153) % | ALL REXULTI (N=503) %
Infections and Infestations
Nasopharyngitis | 2 | 4 | 2 | 3 | 3
Urinary Tract Infection | 1 | 2 | 3 | 3 | 3
Nervous System Disorders
Dizziness [Dizziness and Vertigo are grouped to Dizziness] | 2 | 1 | 5 | 3 | 3
Headache | 8 | 9 | 9 | 7 | 8
Somnolence [Sedation and somnolence are grouped to somnolence.] | 1 | 2 | 3 | 4 | 3
Psychiatric Disorders
Insomnia [Initial insomnia and insomnia are grouped to insomnia] | 3 | 5 | 5 | 2 | 4

Extrapyramidal Symptoms

Adjunctive Treatment of Major Depressive Disorder

The incidence of reported extrapyramidal symptoms (EPS)-related adverse reactions, excluding akathisia, was 6% for REXULTI plus ADT-treated patients versus 3% for placebo plus ADT-treated patients. The incidence of akathisia events for REXULTI plus ADT-treated patients was 9% versus 2% for placebo plus ADT-treated patients.

In the 6-week placebo-controlled MDD studies, data was objectively collected on the Simpson-Angus Rating Scale (SAS) for EPS, the Barnes Akathisia Rating Scale (BARS) for akathisia and the Abnormal Involuntary Movement Score (AIMS) for dyskinesia. The mean change from baseline at last visit for REXULTI plus ADT-treated patients for the SAS, BARS and AIMS was comparable to placebo-treated patients. The percentage of patients who shifted from normal to abnormal was greater in REXULTI plus ADT-treated patients versus placebo plus ADT-treated patients for the BARS (4% versus 0.6%) and the SAS (4% versus 3%).

Schizophrenia(Adults)

The incidence of reported EPS-related adverse reactions, excluding akathisia, was 5% for REXULTI-treated adult patients versus 4% for placebo-treated patients. The incidence of akathisia events for REXULTI-treated adult patients was 6% versus 5% for placebo-treated patients.

In the 6-week placebo-controlled, fixed-dose schizophrenia studies in adults, data was objectively collected on the Simpson-Angus Rating Scale (SAS) for EPS, the Barnes Akathisia Rating Scale (BARS) for akathisia and the Abnormal Involuntary Movement Scale (AIMS) for dyskinesia. The mean change from baseline at last visit for REXULTI-treated patients for the SAS, BARS and AIMS was comparable to placebo-treated patients. The percentage of patients who shifted from normal to abnormal was greater in REXULTI-treated patients versus placebo for the BARS (2% versus 1%) and the SAS (7% versus 5%).

Schizophrenia [Pediatric Patients (13 to 17 years of age)]

The incidence of reported EPS-related adverse reactions, excluding akathisia, was 6.4% for REXULTI-treated pediatric patients versus 2.9% for placebo-treated patients. The incidence of akathisia events for REXULTI-treated pediatric patients was 3.6% versus 2.9% for placebo-treated patients.

In the 6-week placebo-and active controlled, schizophrenia study in pediatric patients, data was objectively collected on the Simpson-Angus Rating Scale (SAS) for EPS, the Barnes Akathisia Rating Scale (BARS) for akathisia and the Abnormal Involuntary Movement Scale (AIMS) for dyskinesia. The mean change from baseline at last visit for REXULTI-treated pediatric patients for the SAS, BARS and AIMS was comparable to placebo-treated patients. The percentage of patients who shifted from normal to abnormal was greater in REXULTI-treated patients versus placebo for the BARS (0.9% versus 0%) and the SAS (5.5% versus 2.9%).

Agitation Associated with Dementia Due to Alzheimer's Disease

The incidence of reported EPS-related adverse reactions, excluding akathisia, was 3% for REXULTI-treated patients versus 2% for placebo-treated patients. The incidence of akathisia events for REXULTI-treated patients was 1% versus 0% for placebo-treated patients.

In the 12-week placebo-controlled, fixed-dose studies in agitation associated with dementia due to Alzheimer's disease, data was objectively collected on the Simpson-Angus Rating Scale (SAS) for EPS, the Barnes Akathisia Rating Scale (BARS) for akathisia and the Abnormal Involuntary Movement Scale (AIMS) for dyskinesia. The mean change from baseline at last visit for REXULTI-treated patients for the SAS, BARS and AIMS was comparable to placebo-treated patients. The percentage of patients who shifted from normal to abnormal was greater in REXULTI-treated patients versus placebo for the SAS (6% versus 2%).

Dystonia

Symptoms of dystonia may occur in susceptible individuals during the first few days of treatment. Dystonic symptoms include spasm of the neck muscles, sometimes progressing to tightness of the throat, swallowing difficulty, difficulty breathing, and/or protrusion of the tongue. While these symptoms can occur at low doses, they occur more frequently and with greater severity with high potency and at higher doses of first-generation antipsychotic drugs. An elevated risk of acute dystonia is observed in males and younger age groups.

Other Adverse Reactions Observed during Clinical Trial Evaluation of REXULTI

Other adverse reactions (≥1% frequency and greater than placebo) within the short-term, placebo-controlled trials in adult patients with MDD and schizophrenia are shown below. The following listing does not include adverse reactions: 1) already listed in previous tables or elsewhere in the labeling, 2) for which a drug cause was remote, 3) which were so general as to be uninformative, 4) which were not considered to have clinically significant implications, or 5) which occurred at a rate equal to or less than placebo.

Eye Disorders: Vision Blurred

Gastrointestinal Disorders: Nausea, Dry Mouth, Salivary Hypersecretion, Abdominal Pain, Flatulence

Investigations: Blood Prolactin Increased

Musculoskeletal and Connective Tissue Disorders: Myalgia

Psychiatric Disorders: Abnormal Dreams

Skin and Subcutaneous Tissue Disorders: Hyperhidrosis

Pediatric Patients (13 to 17 years of age)

In a short-term, randomized, double-blind, placebo- controlled study in pediatric patients 13 to 17 years of age with schizophrenia, safety was assessed in 110 patients in which 100 received REXULTI for at least 6 weeks. In an on-going, 2 year, open-label study in pediatric patients 13 to 17 years of age with schizophrenia, in which safety was assessed in 194 patients of which 140 received REXULTI for at least 6 months. Adverse reactions reported in clinical studies for this age group were generally similar to those observed in adult patients.

Hyperprolactinemia

In a 6-week, placebo-controlled study in pediatric patients with schizophrenia, a 3.3 ng/mL mean increase (from baseline to last visit) was observed in the REXULTI group (versus a 2.8 ng/mL mean decrease in the placebo group) in females. Additionally, more female subjects in the REXULTI group (28.9%, n=13) compared to the placebo group (4.7%, n=2) had shifts from normal (≤30 ng/mL) prolactin levels at baseline to abnormal (>30 ng/mL) during the course of treatment. In males, overall mean shifts in the REXULTI group were not consistent with an increase in prolactin however, more male subjects in the REXULTI group (21.4%, n=9) compared to the placebo group (7.0%, n=3) had shifts from normal (≤20 ng/mL) prolactin levels at baseline to abnormal (>20 ng/mL) during the course of treatment. One subject in the study experienced TEAE of galactorrhea without elevated prolactin.

6.2 Postmarketing Experience

The following adverse reaction has been identified during post-approval use of REXULTI. Because these reactions are reported voluntarily from a population of uncertain size, it is not always possible to reliably estimate their frequency or establish a causal relationship to drug exposure.

Nervous System disorders: Neuroleptic Malignant Syndrome

7 DRUG INTERACTIONS

7.1 Drugs Having Clinically Important Interactions with REXULTI

See Table 12 for clinically important drug interactions with REXULTI.

Table 12 Clinically Important Drug Interactions with REXULTI
Strong CYP3A4 Inhibitors
Clinical Impact: | Concomitant use of REXULTI with strong CYP3A4 inhibitors increased the exposure of brexpiprazole compared to the use of REXULTI alone [see Clinical Pharmacology (12.3)].
Intervention: | With concomitant use of REXULTI with a strong CYP3A4 inhibitor, reduce the REXULTI dosage [see Dosage and Administration (2.7)].
Strong CYP2D6 Inhibitors [In the clinical studies examining the adjunctive use of REXULTI in the treatment of MDD, dosage was not adjusted for strong CYP2D6 inhibitors (e.g., paroxetine, fluoxetine). Thus, CYP considerations are already factored into general dosing recommendations, and REXULTI may be administered without dosage adjustment in patients with MDD.]
Clinical Impact: | Concomitant use of REXULTI with strong CYP2D6 inhibitors increased the exposure of brexpiprazole compared to the use of REXULTI alone [see Clinical Pharmacology (12.3)].
Intervention: | With concomitant use of REXULTI with a strong CYP2D6 inhibitor, reduce the REXULTI dosage [see Dosage and Administration (2.7)].
Both CYP3A4 Inhibitors and CYP2D6 Inhibitors
Clinical Impact: | Concomitant use of REXULTI with 1) a strong CYP3A4 inhibitor and a strong CYP2D6 inhibitor; or 2) a moderate CYP3A4 inhibitor and a strong CYP2D6 inhibitor; or 3) a strong CYP3A4 inhibitor and a moderate CYP2D6 inhibitor; or 4) a moderate CYP3A4 inhibitor and a moderate CYP2D6 inhibitor increased the exposure of brexpiprazole compared to the use of REXULTI alone [see Clinical Pharmacology (12.3)].
Intervention: | With concomitant use of REXULTI with 1) a strong CYP3A4 inhibitor and a strong CYP2D6 inhibitor; or 2) a moderate CYP3A4 inhibitor and a strong CYP2D6 inhibitor; or 3) a strong CYP3A4 inhibitor and a moderate CYP2D6 inhibitor; or 4) a moderate CYP3A4 inhibitor and a moderate CYP2D6 inhibitor, decrease the REXULTI dosage [see Dosage and Administration (2.7)].
Strong CYP3A4 Inducers
Clinical Impact: | Concomitant use of REXULTI and a strong CYP3A4 inducer decreased the exposure of brexpiprazole compared to the use of REXULTI alone [see Clinical Pharmacology (12.3)].
Intervention: | With concomitant use of REXULTI with a strong CYP3A4 inducer, increase the REXULTI dosage [see Dosage and Administration (2.7)].

7.2 Drugs Having No Clinically Important Interactions with REXULTI

Based on pharmacokinetic studies, no dosage adjustment of REXULTI is required when administered concomitantly with CYP2B6 inhibitors (e.g., ticlopidine) or gastric pH modifiers (e.g., omeprazole). Additionally, no dosage adjustment for substrates of CYP2D6 (e.g., dextromethorphan), CYP3A4 (e.g., lovastatin), CYP2B6 (e.g., bupropion), BCRP (e.g., rosuvastatin), or P-gp (e.g., fexofenadine) is required when administered concomitantly with REXULTI.

8 USE IN SPECIFIC POPULATIONS

8.1 Pregnancy

Pregnancy Exposure Registry

There is a pregnancy exposure registry that monitors pregnancy outcomes in women exposed to REXULTI during pregnancy. For more information contact the National Pregnancy Registry for Psychiatric Medications at 1-866-961-2388 or visit http://womensmentalhealth.org/clinical-and-research-programs/pregnancyregistry/.

Risk Summary

Adequate and well-controlled studies have not been conducted with REXULTI in pregnant women to inform drug-associated risks. However, neonates whose mothers are exposed to antipsychotic drugs, like REXULTI, during the third trimester of pregnancy are at risk for extrapyramidal and/or withdrawal symptoms. In animal reproduction studies, no teratogenicity was observed with oral administration of brexpiprazole to pregnant rats and rabbits during organogenesis at doses up to 73 and 146 times, respectively, of maximum recommended human dose (MRHD) of 4 mg/day on a mg/m^2 basis. However, when pregnant rats were administered brexpiprazole during the period of organogenesis through lactation, the number of perinatal deaths of pups was increased at 73 times the MRHD [see Data]. The background risk of major birth defects and miscarriage for the indicated population(s) is unknown. In the U.S. general population, the estimated background risk of major birth defects and miscarriage in clinically recognized pregnancies is 2 to 4% and 15 to 20%, respectively.

Clinical Considerations

Fetal/Neonatal Adverse Reactions

Extrapyramidal and/or withdrawal symptoms, including agitation, hypertonia, hypotonia, tremor, somnolence, respiratory distress and feeding disorder, have been reported in neonates whose mothers were exposed to antipsychotic drugs during the third trimester of pregnancy. These symptoms have varied in severity. Some neonates recovered within hours or days without specific treatment; others required prolonged hospitalization. Monitor neonates for extrapyramidal and/or withdrawal symptoms and manage symptoms appropriately.

Data

Animal Data

Pregnant rats were treated with oral doses of 3, 10, and 30 mg/kg/day (7.3, 24, and 73 times the MRHD on a mg/m^2 basis) of brexpiprazole during the period of organogenesis. Brexpiprazole was not teratogenic and did not cause adverse developmental effects at doses up to 73 times the MRHD.

Pregnant rabbits were treated with oral doses of 10, 30, and 150 mg/kg/day (49, 146, and 730 times the MRHD) of brexpiprazole during the period of organogenesis. Brexpiprazole was not teratogenic and did not cause adverse developmental effects at doses up to 146 times the MRHD. Findings of decreased body weight, retarded ossification, and increased incidences of visceral and skeletal variations were observed in fetuses at 730 times the MRHD, a dose that induced maternal toxicity.

In a study in which pregnant rats were administered oral doses of 3, 10, and 30 mg/kg/day (7.3, 24, and 73 times the MRHD) during the period of organogenesis and through lactation, the number of live-born pups was decreased, and early postnatal deaths increased at a dose 73 times the MRHD. Impaired nursing by dams, and low birth weight and decreased body weight gain in pups were observed at 73 times, but not at 24 times, the MRHD.

8.2 Lactation

Risk Summary

Lactation studies have not been conducted to assess the presence of brexpiprazole in human milk, the effects of brexpiprazole on the breastfed infant, or the effects of brexpiprazole on milk production. Brexpiprazole is present in rat milk. The development and health benefits of breastfeeding should be considered along with the mother's clinical need for REXULTI and any potential adverse effects on the breastfed infant from REXULTI or from the underlying maternal condition.

8.4 Pediatric Use

Schizophrenia

The safety and effectiveness of REXULTI for treatment of schizophrenia have been established in pediatric patients 13 years of age and older. Use of REXULTI in this population is supported by evidence from adequate and well-controlled studies in adults and pediatric patients with schizophrenia, pharmacokinetic data from adults and pediatric patients, and safety data in pediatric patients 13 to 17 years of age [see Warnings and Precautions (5.6), Adverse Reactions (6.1), Clinical Pharmacology (12.3), Clinical Studies (14.2)].

The safety and effectiveness of REXULTI for the treatment of schizophrenia have not been established in pediatric patients less than 13 years of age.

Major Depressive Disorder

The safety and effectiveness of REXULTI for treatment of major depressive disorder have not been established in pediatric patients. Antidepressants increased the risk of suicidal thoughts and behaviors in pediatric patients [see Boxed Warning, Warnings and Precautions (5.2)].

Irritability Associated with Autism Spectrum Disorder

The safety and effectiveness of REXULTI for the treatment of irritability associated with autism spectrum disorder have not been established in pediatric patients. Effectiveness was not demonstrated, in an 8-week, double-blind, placebo-controlled, flexible-dose clinical study conducted in 119 REXULTI-treated pediatric patients 5 to 17 years of age with irritability associated with autism spectrum disorder diagnosed by the Diagnostic and Statistical Manual of Mental Disorders, 5th Edition [DSM-5] criteria. In this study, somnolence (including sedation) occurred at a higher rate than reported in other REXULTI studies evaluating adults and elderly patients (16% in REXULTI-treated pediatric patients versus 5% for placebo). The mean increase in age-and-gender adjusted body weight z-score from baseline to last visit was 0.3 for REXULTI-treated patients versus 0.1 for placebo-treated patients. Increases in age-and-gender adjusted body weight z-score of at least 0.5 SD from baseline was higher in REXULTI-treated patients versus placebo (19% versus 5%).

Of the 119 patients from this study, 95 patients entered the open-label treatment study and received up to 26 weeks of daily treatment with brexpiprazole. During the open-label treatment period, 2% of patients discontinued due to weight increase. In patients previously treated with REXULTI for 8 weeks, the mean increase in weight from the open-label study baseline to last visit was 4.5 kg. and 26% of patients had an increase in age-and-gender-adjusted body weight z-score of at least 0.5 SD from baseline.

Juvenile Animal Studies

Juvenile rats were administered oral doses of brexpiprazole of 3, 10, and 20 mg/kg/day once daily beginning from weaning (postnatal day 21) through adulthood (postnatal day 90), followed by a 4-week recovery (non-dosing) period. Results were similar to those observed in previous repeat‑dose toxicity studies in adolescent (8-week-old) rats. Mortality occurred at the high-dose of 20 mg/kg/day, as well as delayed sexual maturation in males and decreased rearing and motor activity. There was no evidence of neurotoxicity or effects on fertility and reproductive function. Histopathologic changes in reproductive organs and mammary glands occurred at all doses, were related to the pharmacology of brexpiprazole and were comparable to those in adult rats. All findings were at least partially reversible. Juvenile dogs were administered oral doses of brexpiprazole of 1, 3, and 30 mg/kg/day once daily starting at 8 or 9 weeks of age for 26 weeks, followed by an 8-week recovery (non-dosing) period. Decreases in body weight, lethargy, changes in heart rate, and immature male sex organs were observed at 30 mg/kg/day. These findings were at least partially reversible.

8.5 Geriatric Use

Antipsychotic drugs increase the risk of death in elderly patients with dementia-related psychosis. REXULTI is not approved for the treatment of patients with dementia-related psychosis [see Boxed Warning, Warnings and Precautions (5.1)].

Adjunctive Treatment of Major Depressive Disorder (MDD) and Schizophrenia

Of the total number of REXULTI-treated patients in the clinical studies for the adjunctive therapy to antidepressants for MDD and for schizophrenia, 248 (3%) were 65 years of age and older (which included 45 (18%) patients who were 75 years of age and older). Clinical studies of REXULTI in these patients did not include sufficient numbers of patients 65 years of age and older to determine whether they respond differently from younger adult patients. In general, dosage selection for the treatment of MDD or schizophrenia in a geriatric patient should be cautious, usually starting at the low end of the dosing range, reflecting the greater frequency of decreased hepatic, renal, and cardiac function, concomitant diseases, and other drug therapy.

Agitation Associated with Dementia Due to Alzheimer's Disease

The total number of REXULTI-treated patients 65 years of age and older in the clinical studies for agitation associated with dementia due to Alzheimer's disease (Studies 6 and 7) was 448 (86%) including 170 (33%) patients 65 to 74 years of age, 228 (44%) patients 75 to 84 years of age, and 50 (10%) patients 85 years of age and older [see Clinical Studies (14.3)].

In clinical studies of REXULTI for the treatment of agitation associated with dementia due to Alzheimer's disease did not include sufficient numbers of younger adult patients to determine if patients 65 years of age and older respond differently than younger adult patients.

8.6 CYP2D6 Poor Metabolizers

Dosage adjustment is recommended in known CYP2D6 poor metabolizers because these patients have higher brexpiprazole concentrations than normal metabolizers of CYP2D6. Approximately 8% of Caucasians and 3 to 8% of Black/African Americans cannot metabolize CYP2D6 substrates and are classified as poor metabolizers [see Dosage and Administration (2.7), Clinical Pharmacology (12.3)].

8.7 Hepatic Impairment

The maximum recommended dosage in patients with moderate to severe hepatic impairment (Child-Pugh score ≥7) is lower than those with mild hepatic impairment and those with normal hepatic function [see Dosage and Administration (2.4)]. Patients with moderate to severe hepatic impairment generally had higher exposure to brexpiprazole than patients with normal hepatic function [see Clinical Pharmacology (12.3)]. Greater exposure may increase the risk of REXULTI-associated adverse reactions .

8.8 Renal Impairment

The maximum recommended dosage in patients with CrCl<60 mL/minute is lower than those with mild renal impairment and those with normal renal function [see Dosage and Administration (2.6)]. Patients with renal impairment had higher exposure to brexpiprazole than patients with normal renal function [see Clinical Pharmacology (12.3)]. Greater exposure may increase the risk of REXULTI-associated adverse reactions.

8.9 Other Specific Populations

The recommended dosage for REXULTI is the same in males and females, in different racial groups, and in smokers and nonsmokers [see Clinical Pharmacology (12.3)].

9 DRUG ABUSE AND DEPENDENCE

9.1 Controlled Substance

REXULTI contains brexpiprazole, which is not a controlled substance.

9.2 Abuse

Animals given access to REXULTI did not self-administer the drug, suggesting that REXULTI does not have rewarding properties.

9.3 Dependence

Humans and animals that received chronic REXULTI administration did not demonstrate any withdrawal signs upon drug discontinuation. This suggests that REXULTI does not produce physical dependence.

10 OVERDOSAGE

There is limited clinical trial experience regarding human overdosage with REXULTI.

Management of a REXULTI overdose should concentrate on supportive therapy, maintaining an adequate airway, oxygenation and ventilation, and management of symptoms. Close medical supervision and monitoring should continue until the patient recovers. Consider contacting the Poison Help Line (1-800-222-1222) or a medical toxicologist for additional overdosage management recommendations.

Oral activated charcoal and sorbitol (50 g/240 mL), administered one hour after ingesting oral REXULTI, decreased brexpiprazole Cmax and area under the curve (AUC) by approximately 5% to 23% and 31% to 39% respectively; however, there is insufficient information available on the therapeutic potential of activated charcoal in treating an overdose with REXULTI.

There is no information on the effect of hemodialysis in treating an overdose with REXULTI; hemodialysis is unlikely to be useful because brexpiprazole is highly bound to plasma proteins.

11 DESCRIPTION

Brexpiprazole, an atypical antipsychotic, is available as REXULTI® (brexpiprazole) tablets. Brexpiprazole is 7-{4-[4-(1-Benzothiophen-4-yl)piperazin-1-yl]butoxy}quinolin-2(1H)-one. The empirical formula is C25H27N3O2S, and its molecular weight is 433.57. The chemical structure is:

REXULTI tablets are for oral administration and are available in 0.25 mg, 0.5 mg, 1 mg, 2 mg, 3 mg, and 4 mg strengths. Inactive ingredients include lactose monohydrate, corn starch, microcrystalline cellulose, hydroxypropyl cellulose, low-substituted hydroxypropyl cellulose, magnesium stearate, hypromellose, and talc. Colorants include titanium dioxide, iron oxide, and ferrosoferric oxide.

12 CLINICAL PHARMACOLOGY

12.1 Mechanism of Action

The mechanism of action of REXULTI in the adjunctive treatment of major depressive disorder, treatment of agitation associated with dementia due to Alzheimer's disease, or treatment of schizophrenia is unknown. However, the efficacy of REXULTI may be mediated through a combination of partial agonist activity at serotonin 5-HT1A and dopamine D2 receptors, and antagonist activity at serotonin 5-HT2A receptors.

12.2 Pharmacodynamics

Brexpiprazole has affinity (expressed as Ki) for multiple monoaminergic receptors including serotonin 5-HT1A (0.12 nM), 5-HT2A (0.47 nM), 5-HT2B (1.9 nM), 5-HT7 (3.7 nM), dopamine D2 (0.30 nM), D3 (1.1 nM), and noradrenergic α1A (3.8 nM), α1B (0.17 nM), α1D (2.6 nM), and α2C (0.59 nM) receptors. Brexpiprazole acts as a partial agonist at the 5-HT1A, D2, and D3 receptors and as an antagonist at 5-HT2A, 5-HT2B, 5-HT7, α1A, α1B, α1D, and α2C receptors. Brexpiprazole also exhibits affinity for histamine H1 receptor (19 nM) and for muscarinic M1 receptor (67% inhibition at 10 µM).

Cardiac Electrophysiology

At a dose 3 times the MRHD for the treatment of schizophrenia and 4 times the MRHD for adjunctive therapy to antidepressants for the treatment of MDD or agitation associated with dementia due to Alzheimer's disease, REXULTI does not prolong the QTc interval to any clinically relevant extent.

12.3 Pharmacokinetics

Absorption

After single-dose administration of REXULTI tablets, the peak plasma brexpiprazole concentrations occurred within 4 hours after administration, and the absolute oral bioavailability was 95%. Brexpiprazole steady-state concentrations were attained within 10 to 12 days of dosing.

REXULTI can be administered with or without food. Administration of a 4 mg REXULTI tablet with a standard high-fat meal did not significantly affect the Cmax or AUC of brexpiprazole. After single and multiple once daily dose administration, brexpiprazole exposure (Cmax and AUC) increased in proportion to the dose administered. In vitro studies of brexpiprazole did not indicate that brexpiprazole is a substrate of efflux transporters such as MDRI (P-gp) and BCRP.

Distribution

The volume of distribution of brexpiprazole following intravenous administration is high (1.56 ± 0.42 L/kg), indicating extravascular distribution. Brexpiprazole is highly protein bound in plasma (greater than 99%) to serum albumin and α1-acid glycoprotein, and its protein binding is not affected by renal or hepatic impairment. Based on results of in vitro studies, brexpiprazole protein binding is not affected by warfarin, diazepam, or digitoxin.

Elimination

Metabolism

Based on in vitro metabolism studies of brexpiprazole using recombinant human cytochrome P450 (CYP1A1, 1A2, 2A6, 2B6, 2C8, 2C9, 2C19, 2D6, 2E1, and 3A4), the metabolism of brexpiprazole was shown to be mainly mediated by CYP3A4 and CYP2D6.

In vivo brexpiprazole is metabolized primarily by CYP3A4 and CYP2D6 enzymes. After single- and multiple-dose administrations, brexpiprazole and its major metabolite, DM-3411, were the predominant drug moieties in the systemic circulation. At steady-state, DM-3411 represented 23% to 48% of brexpiprazole exposure (AUC) in plasma. DM-3411 is considered not to contribute to the therapeutic effects of brexpiprazole.

Based on in vitro data, brexpiprazole showed little to no inhibition of CYP450 isozymes.

Excretion

Following a single oral dose of [^14C]-labeled brexpiprazole, approximately 25% and 46% of the administered radioactivity was recovered in the urine and feces, respectively. Less than 1% of unchanged brexpiprazole was excreted in the urine, and approximately 14% of the oral dose was recovered unchanged in the feces. Apparent oral clearance of a brexpiprazole oral tablet after once daily administration is 19.8 (±11.4) mL/h/kg. After multiple once-daily administrations of REXULTI, the terminal elimination half-lives of brexpiprazole and its major metabolite, DM-3411, were 91 hours and 86 hours, respectively.

Studies in Specific Populations

Exposure of brexpiprazole in specific populations are summarized in Figure 1. Population pharmacokinetic (PK) analysis indicated exposure of brexpiprazole in patients with moderate renal impairment was higher compared to patients with normal renal function.

Figure 1 The Effect of Intrinsic Factors on Brexpiprazole Pharmacokinetics

Pediatric Patients

A multiple dose PK study (0.5, 1, 2, 3 or 4 mg/day) has been conducted in 43 pediatric patients aged 13 years to 17 years old. Population PK analysis indicated systemic exposure (Cmax and AUC) of brexpiprazole in pediatric patients (13 to 17 years of age) was comparable to that in adult patients across the dose range from 0.5 to 4 mg.

Drug Interaction Studies

Effect of other drugs on the exposures of brexpiprazole are summarized in Figure 2. Based on simulation, a 5.1-fold increase in AUC values at steady-state is expected when extensive metabolizers of CYP2D6 are administered with both strong CYP2D6 and CYP3A4 inhibitors. A 4.8-fold increase in mean AUC values at steady-state is expected in poor metabolizers of CYP2D6 administered with strong CYP3A4 inhibitors [see Drug Interactions (7.1)].

Figure 2 The Effect of Other Drugs on Brexpiprazole Pharmacokinetics

The effect of REXULTI on the exposures of other drugs are summarized in Figure 3.

Figure 3 The Effect of REXULTI on Pharmacokinetics of Other Drugs

13 NONCLINICAL TOXICOLOGY

13.1 Carcinogenesis, Mutagenesis, Impairment of Fertility

Carcinogenesis

Lifetime carcinogenicity studies were conducted in ICR mice and Sprague Dawley rats. Brexpiprazole was administered orally for two years to male and female mice at doses of 0.75, 2, and 5 mg/kg/day (0.9 to 6.1 times the oral MRHD of 4 mg/day based on mg/m^2 body surface area) and to male and female rats at doses of 1, 3, and 10 mg/kg and 3, 10, and 30 mg/kg/day, respectively (2.4 to 24 and 7.3 to 73 times the oral MRHD, males and females). In female mice, the incidence of mammary gland adenocarcinoma was increased at all doses, and the incidence of adenosquamous carcinoma was increased at 2.4 and 6.1 times the MRHD. No increase in the incidence of tumors was observed in male mice. In the rat study, brexpiprazole was not carcinogenic in either sex at doses up to 73 times the MRHD.

Proliferative and/or neoplastic changes in the mammary and pituitary glands of rodents have been observed following chronic administration of antipsychotic drugs and are considered to be prolactin mediated. The potential for increasing serum prolactin level of brexpiprazole was shown in both mice and rats. The relevance for human risk of the findings of prolactin-mediated endocrine tumors in rodents is unknown.

Mutagenesis

Brexpiprazole was not mutagenic when tested in the in vitro bacterial reverse mutation assay (Ames test). Brexpiprazole was negative for clastogenic activity in the in vivo micronucleus assay in rats and was not genotoxic in the in vivo/in vitro unscheduled DNA synthesis assay in rats. In vitro with mammalian cells brexpiprazole was clastogenic but only at doses that induced cytotoxicity. Based on a weight of evidence, brexpiprazole is not considered to present a genotoxic risk to humans.

Impairment of Fertility

Female rats were treated with oral doses of 0.3, 3, or 30 mg/kg/day (0.7, 7.3, and 73 times the oral MRHD on a mg/m^2 basis) prior to mating with untreated males and continuing through conception and implantation. Estrus cycle irregularities and decreased fertility were observed at 3 and 30 mg/kg/day. Prolonged duration of pairing and increased preimplantation losses were observed at 30 mg/kg/day.

Male rats were treated with oral doses of 3, 10, or 100 mg/kg/day (7.3, 24, and 240 times the oral MRHD on a mg/m^2 basis) for 63 days prior to mating with untreated females and throughout the 14 days of mating. No differences were observed in the duration of mating or fertility indices in males at any dose of brexpiprazole.

14 CLINICAL STUDIES

14.1 Adjunctive Treatment of Major Depressive Disorder

The efficacy of REXULTI in the adjunctive treatment of major depressive disorder (MDD) was evaluated in two 6-week double-blind, placebo-controlled, fixed-dose studies of adult patients meeting DSM-IV-TR criteria for MDD, with or without symptoms of anxiety, who had an inadequate response to prior antidepressant therapy (1 to 3 courses) in the current episode and who had also demonstrated an inadequate response throughout the 8 weeks of prospective antidepressant treatment (with escitalopram, fluoxetine, paroxetine controlled-release, sertraline, duloxetine delayed release, or venlafaxine extended release). Inadequate response during the prospective antidepressant treatment phase was defined as having persistent symptoms without substantial improvement throughout the course of treatment.

Patients in Study 1 (NCT01360645) were randomized to REXULTI 2 mg once a day or placebo. Patients in Study 2 (NCT01360632) were randomized to REXULTI 1 or 3 mg once a day or placebo. For patients randomized to REXULTI, all patients initiated treatment at 0.5 mg once daily during Week 1. At Week 2, the REXULTI dosage was increased to 1 mg in all treatment groups, and either maintained at 1 mg or increased to 2 mg or 3 mg once daily, based on treatment assignment, from Week 3 onwards. The dosages were then maintained for the 4 remaining weeks.

The primary endpoint was change from baseline to Week 6 in the Montgomery-Asberg Depression Rating Scale (MADRS), a 10-item clinician-related scale used to assess the degree of depressive symptomatology, with 0 representing no symptoms and 60 representing worst symptoms.

At randomization, the mean MADRS total score was 27. In Studies 1 and 2, REXULTI (plus ADT) 2 mg once daily and 3 mg once daily were superior to placebo plus ADT in reducing mean MADRS total scores. Results from the primary efficacy parameters for both fixed dose studies are shown below in Table 13. Figure 4 below shows the time course of response based on the primary efficacy measure (MADRS) in Study 1.

Table 13 Change in MADRS from Baseline at Week 6 in Adult Patients for Adjunctive Treatment of MDD (Study 1 and Study 2)
Study | Treatment Group | N | Mean Baseline Score (SD) | LS Mean Change from Baseline (SE) | Placebo-subtracted Difference [Difference (drug minus placebo) in least-squares mean change from baseline] (95% CI)
1 | REXULTI (2 mg/day) + ADT [Dosages statistically significantly superior to placebo] | 175 | 26.9 (5.7) | -8.4 (0.6) | -3.2 (-4.9, -1.5)
 | Placebo + ADT | 178 | 27.3 (5.6) | -5.2 (0.6) | --
2 | REXULTI (1 mg/day) + ADT | 211 | 26.5 (5.6) | -7.6 (0.5) | -1.3 (-2.7, 0.1)
 | REXULTI (3 mg/day) + ADT | 213 | 26.5 (5.3) | -8.3 (0.5) | -2.0 (-3.4, -0.5)
 | Placebo + ADT | 203 | 26.5 (5.2) | -6.3 (0.5) | --
SD: standard deviation; SE: standard error; LS Mean: least-squares mean; CI: unadjusted confidence interval

An examination of population subgroups did not suggest differential response based on age, gender, race, or choice of prospective antidepressant.

Figure 4 Change from Baseline in MADRS Total Score by Study Visit (Week) in Patients with MDD in Adults (Study 1)

14.2 Schizophrenia

Adult Patients

The efficacy of REXULTI in the treatment of adults with schizophrenia was demonstrated in two 6-week randomized, double-blind, placebo-controlled, fixed-dose clinical studies in patients who met DSM-IV-TR criteria for schizophrenia.

In both studies, Study 3 (NCT01396421) and Study 4 (NCT01393613), patients were randomized to REXULTI 2 or 4 mg once per day or placebo. Patients in the REXULTI groups initiated treatment at 1 mg once daily on Days 1 to 4. The REXULTI dosage was increased to 2 mg on Days 5 to 7. The dosage was then either maintained at 2 mg once daily or increased to 4 mg once daily, depending on treatment assignment, for the 5 remaining weeks.

The primary efficacy endpoint of both studies was the change from baseline to Week 6 in the Positive and Negative Syndrome Scale (PANSS) total score. The PANSS is a 30-item scale that measures positive symptoms of schizophrenia (7 items), negative symptoms of schizophrenia (7 items), and general psychopathology (16 items), each rated on a scale of 1 (absent) to 7 (extreme); the total PANSS scores range from 30 (best) to 210 (worst).

In Study 3, REXULTI at both 2 mg once daily and 4 mg once daily was superior to placebo on the PANSS total score. In Study 4, REXULTI 4 mg once daily was superior to placebo on the PANSS total score (Table 14). Figure 5 shows the time course of response based on the primary efficacy measure (change from baseline in PANSS total score) in Study 3.

Examination of population subgroups based on age, sex, and race did not suggest differential responsiveness.

Table 14 Change in PANSS Total Score from Baseline at Week 6 in Adult Patients in Studies of Schizophrenia (Study 3 and Study 4)
Study | Treatment Group | N | Mean Baseline Score (SD) | LS Mean Change from Baseline (SE) | Placebo-subtracted Difference [Difference (drug minus placebo) in least-squares mean change from baseline] (95% CI)
3 | REXULTI (2 mg/day) [Dosages statistically significantly superior to placebo] | 180 | 95.9 (13.8) | -20.7 (1.5) | -8.7 (-13.1, -4.4)
3 | REXULTI (4 mg/day) | 178 | 94.7 (12.1) | -19.7 (1.5) | -7.6 (-12.0, -3.1)
3 | Placebo | 178 | 95.7 (11.5) | -12.0 (1.6) | --
4 | REXULTI (2 mg/day) | 179 | 96.3 (12.9) | -16.6 (1.5) | -3.1 (-7.2, 1.1)
4 | REXULTI (4 mg/day) | 181 | 95.0 (12.4) | -20.0 (1.5) | -6.5 (-10.6, -2.4)
4 | Placebo | 180 | 94.6 (12.8) | -13.5 (1.5) | --
SD: standard deviation; SE: standard error; LS Mean: least-squares mean; CI: unadjusted confidence interval

Figure 5 Change from Baseline in PANSS Total Score by Study Visit (Week) in Adult Patients with Schizophrenia (Study 3)

The safety and efficacy of REXULTI as maintenance treatment in adults with schizophrenia aged 18 to 65 years were demonstrated in the maintenance phase of a randomized withdrawal study (Study 5, NCT01668797). Patients were stabilized for at least 12 weeks on 1 to 4 mg/day of REXULTI (N=202). They were then randomized in the double-blind treatment phase to either continue REXULTI at their achieved stable dose (N=97), or to switch to placebo (N=105).

The primary endpoint in Study 5 was time from randomization to impending relapse during the double-blind phase, defined as: 1) Clinical Global Improvement score of ≥5 (minimally worse) and an increase to a score >4 on PANSS conceptual disorganization, hallucinatory behavior, suspiciousness, or unusual thought content items, with either a ≥2 increase on a specific item or ≥4 point increase on the combined four PANSS items, 2) hospitalization due to worsening of psychotic symptoms, 3) current suicidal behavior, or 4) violent/aggressive behavior.

A pre-specified interim analysis demonstrated a statistically significantly longer time to relapse in patients randomized to the REXULTI group compared to placebo-treated patients. The study was subsequently terminated early because maintenance of efficacy had been demonstrated. The Kaplan-Meier curves of the cumulative proportion of patients with relapse during the double-blind treatment phase for REXULTI and placebo groups are shown in Figure 6. The key secondary endpoint, the proportion of patients who met the criteria for impending relapse, was statistically significantly lower in REXULTI-treated patients compared with placebo group.

Figure 6 Kaplan-Meier Estimation of Percent Impending Relapse in Study 5

Note: A total of 202 patients were randomized. Among them, one patient in the placebo group did not take investigational medicinal product and one patient in the REXULTI group did not have post-randomization efficacy evaluations. These two patients were excluded from the efficacy analysis.

Pediatric Patients Ages 13 to 17 years

The efficacy of REXULTI in the treatment of schizophrenia in pediatric patients 13 to 17 years of age was demonstrated in a 6-week, randomized and placebo-controlled, clinical study.

In Study 6 (NCT03198078), patients were randomized to REXULTI 2 mg to 4 mg once per day, active comparator, or placebo. Patients in the REXULTI group initiated treatment at 0.5 mg once daily on Days 1 to 4. The REXULTI dosage was increased to 1 mg daily on Days 5 to 7, and then increased to 2 mg on Days 8 to 14. The dosage was then either maintained at 2 mg or increased to 3 mg once daily from Days 15 to 21 based on patient's tolerability or clinical response. After the titration period, patients were either kept at a maintenance dose, or increased or decreased by 1 mg, for a maximum of REXULTI 4 mg daily.

The primary efficacy endpoint was the change from baseline to Week 6 in the PANSS total score.

In Study 6, REXULTI group showed a statistically significant improvement compared to placebo on the mean change from baseline in the PANSS total score (Table 15).

Figure 7 shows the time course of response based on the primary efficacy measure (change from baseline in PANSS total score) in Study 6.

Table 15 Change in PANSS Total Score from Baseline at Week 6 in Pediatric Patients 13 to 17 years of age in Study of Schizophrenia (Study 6)
Study | Treatment Group | N [Efficacy sample includes treated subjects who have baseline and at least 1 post-baseline efficacy evaluation for the PANSS Total Score] | Mean Baseline Score (SD) | LS Mean Change from Baseline (SE) | Placebo-subtracted Difference [Difference (drug minus placebo) in least-squares mean change from baseline] (95% CI)
6 | REXULTI (2 - 4 mg/day) [Dosages statistically significantly superior to placebo] | 110 | 101.1 (14.9) | -22.8 (1.5) | -5.3 (-9.6, -1.1)
6 | Placebo | 103 | 102.2 (16.3) | -17.4 (1.6) | --
SD: standard deviation; SE: standard error; LS Mean: least-squares mean; CI: confidence interval

Figure 7 Change from Baseline in PANSS Total Score by Study Visit (Week) in Pediatric Patients 13 to 17 years of age with Schizophrenia (Study 6)

14.3 Agitation Associated with Dementia Due to Alzheimer's Disease

The efficacy of REXULTI in the treatment of agitation associated with dementia due to Alzheimer's disease was demonstrated in two 12-week, randomized, double-blind, placebo-controlled, fixed-dose studies (Study 6, NCT01862640 and Study 7, NCT03548584). In these studies, patients were required to:

- Have a diagnosis of probable Alzheimer's disease according to NINCDS-ADRDA criteria,
- Have a Mini-Mental State Examination (MMSE) score of ≥5 and ≤22 and have a total score of ≥4 by the agitation/aggression item of the NPI/NPI-NH, and
- Exhibit sufficient agitation behaviors at time of entry to warrant use of pharmacotherapy, after excluding other factors.

Patients in:

- Study 6 were randomized to an oral dosage of either REXULTI 1 mg once a day, REXULTI 2 mg once a day, or placebo. Patients in both REXULTI groups started on 0.25 mg once daily for approximately three days, then received 0.5 mg once daily for approximately 12 days. Subsequently, patients in the 1 mg group received 1 mg once daily for the remainder of the 12-week study, and patients in the 2 mg group received 1 mg once daily for approximately two weeks and then received 2 mg for the remainder of the study.
- Study 7 were randomized to an oral dose of either REXULTI 2 mg or 3 mg once a day (combined treatment arm) or placebo. Patients in both REXULTI groups started on 0.5 mg once daily for 7 days, then received 1 mg once daily for 7 days and then 2 mg once daily for 14 days. Subsequently, patients in the 2 mg group received 2 mg once daily for the remainder of the 12-week study, and patients in the 3 mg group received 3 mg once daily for the remainder of the study.

Study 6 included 433 patients with a mean age of 74 years old, and a range of 51 and 90 years old; 45% were male; 96%, 3%, and 1%, were White, Black or African American, and Asian, respectively; and 16% and 83% were Latino/Hispanic and not Latino/Hispanic, respectively. Study 7 included 345 patients with a mean age of 74 years old, and a range of 56 and 90 years old; 44% were male; 95%, 4%, and 1% were White, Black or African American, and Asian, respectively; and 31% and 69% were Latino/Hispanic and not Latino/Hispanic, respectively.

The primary efficacy endpoint in these two studies was the change from baseline in the Cohen-Mansfield Agitation Inventory total (CMAI) score at Week 12. The CMAI is a clinician rated questionnaire consisting of 29 items, which assess the frequency of manifestations of agitated behaviors in elderly patients, based on caregiver input. Three specific factors can be derived from the CMAI scale: 1) Aggressive Behavior (e.g., screaming, throwing things, cursing/verbal aggression, kicking, pushing scratching, hurting self or others); 2) Physically Non-Aggressive Behavior (e.g., repetitive mannerisms, general restlessness, pacing); and 3) Verbally Agitated Behavior (e.g., complaining, repetitive questions, constant requests for attention). Each CMAI behavior was rated on a scale of 1 (never) to 7 (very frequent agitated behaviors); the total CMAI scores range from 29 (best) to 203 (worst). A negative change indicates improvement.

In Trial 6, patients in the REXULTI 2 mg group showed improved total CMAI scores compared to patients in the placebo group at Week 12. In Trial 7, patients in the REXULTI 2 mg/3 mg group showed improved total CMAI scores compared to patients in the placebo group at Week 12.

As shown in Table 16 and Figure 8, the mean change from baseline in the total CMAI score after 12 weeks in the 2 mg/or 3 mg REXULTI group was statistically significantly superior to the placebo group. The 1 mg REXULTI group did not demonstrate significantly greater mean changes at baseline from the placebo group in the total CMAI score in this patient population. The 1 mg once day REXULTI dosage is not approved and is not recommended for the treatment of agitation associated with dementia due to Alzheimer's disease [see Dosage and Administration (2.4)].

Table 16: Change in CMAI Total Score [In a supplementary analysis to examine the magnitude and direction of CMAI subscale response, Factor 1 (aggressive behavior), Factor 2 (physically non-aggressive behavior), and Factor 3 (verbal agitation) scores trended in the same direction with no single factor overly influencing the CMAI total score.] from Baseline at Week 12 in Patients with Agitation Associated with Dementia Due to Alzheimer's Disease (Study 6 and Study 7)
Study | Treatment Group | N | Mean Baseline Score (SD) | LS Mean Change from Baseline (SE) | Placebo-subtracted Difference [Difference (drug minus placebo) in least-squares mean change from baseline] (95% CI)
6 | REXULTI 1 mg/day | 134 | 70.5 (16.0) | -17.6 (1.3) | 0.2 (-3.4, 3.9)
6 | REXULTI 2 mg/day [Dosages statistically significantly superior to placebo.] | 138 | 71.0 (16.6) | -21.6 (1.3) | -3.8 (-7.4, -0.2)
6 | Placebo | 131 | 72.2 (17.9) | -17.8 (1.3) | —
7 | REXULTI 2 mg/day or 3 mg/day | 225 | 80.6 (16.6) | -22.6 (1.1) | -5.3 (-8.8, -1.9)
7 | Placebo | 116 | 79.2 (17.5) | -17.3 (1.4) | —
SD: standard deviation; SE: standard error; LS Mean: least-squares mean; CI: unadjusted confidence interval

Figure 8: Change from Baseline in Total CMAI Score by Study Week in Patients with Agitation Associated with Dementia Due to Alzheimer's Disease (Study 7)

16 HOW SUPPLIED/STORAGE AND HANDLING

How Supplied

REXULTI (brexpiprazole) tablets have markings on one side and are available in the following strengths and package configurations (see below):

- 0.25 mg tablets are light brown, round, shallow convex, bevel-edged body with "BRX" and "0.25" imprinted on one side
  NDC 59148-035-13 | Bottles of 30

- 0.5 mg tablets: are light orange, round, shallow convex, bevel-edged body with "BRX" and "0.5" imprinted on one side
  NDC 59148-036-13 | Bottles of 30

- 1 mg tablets are light yellow, round, shallow convex, bevel-edged body with "BRX" and "1" imprinted on one side
  NDC 59148-037-13 | Bottles of 30

- 2 mg tablets are light green, round, shallow convex, bevel-edged body with "BRX" and "2" imprinted on one side
  NDC 59148-038-13 | Bottles of 30

- 3 mg tablets are light purple, round, shallow convex, bevel-edged body with "BRX" and "3" imprinted on one side
  NDC 59148-039-13 | Bottles of 30

- 4 mg tablets are white, round, shallow convex, bevel-edged body with "BRX" and "4" imprinted on one side
  NDC 59148-040-13 | Bottles of 30

Storage

Store REXULTI tablets at 20°C to 25°C (68°F to 77°F); excursions permitted to 15°C to 30°C (59°F to 86°F) [see USP Controlled Room Temperature].

17 PATIENT COUNSELING INFORMATION

Advise the patient or caregiver to read the FDA-approved patient labeling (Medication Guide).

Suicidal Thoughts and Behaviors

Advise patients and caregivers to look for the emergence of suicidality, especially early during treatment and when the dosage is adjusted up or down, and instruct them to report such symptoms to the healthcare provider [see Boxed Warning, Warnings and Precautions (5.2)].

Dosage and Administration

Advise patients that REXULTI can be taken with or without food. Advise patients regarding importance of following dosage escalation instructions [see Dosage and Administration (2)].

Neuroleptic Malignant Syndrome (NMS)

Counsel patients about a potentially fatal adverse reaction, Neuroleptic Malignant Syndrome (NMS), that has been reported in association with administration of antipsychotic drugs. Advise patients to contact a healthcare provider or report to the emergency room if they experience signs or symptoms of NMS [see Warnings and Precautions (5.4)].

Tardive Dyskinesia

Counsel patients on the signs and symptoms of tardive dyskinesia and to contact their healthcare provider if these abnormal movements occur [see Warnings and Precautions (5.5)].

Metabolic Changes

Educate patients about the risk of metabolic changes, how to recognize symptoms of hyperglycemia and diabetes mellitus, and the need for specific monitoring, including blood glucose, lipids, and weight [see Warnings and Precautions (5.6)].

Pathological Gambling and Other Compulsive Behaviors

Advise patients and their caregivers of the possibility that they may experience compulsive urges to shop, intense urges to gamble, compulsive sexual urges, binge eating and/or other compulsive urges and the inability to control these urges while taking REXULTI. In some cases, but not all, the urges were reported to have stopped when the dose was reduced or stopped [see Warnings and Precautions (5.7)].

Leukopenia, Neutropenia and Agranulocytosis

Advise patients with a pre-existing low WBC or a history of drug-induced leukopenia/neutropenia that they should have their CBC monitored while taking REXULTI [see Warnings and Precautions (5.8)].

Orthostatic Hypotension and Syncope

Educate patients about the risk of orthostatic hypotension and syncope, especially early in treatment, and also at times of reinitiating treatment or increases in dosage [see Warnings and Precautions (5.9)].

Heat Exposure and Dehydration

Counsel patients regarding appropriate care in avoiding overheating and dehydration [see Warnings and Precautions (5.12)].

Potential for Cognitive and Motor Impairment

Caution patients about performing activities requiring mental alertness, such as operating hazardous machinery or operating a motor vehicle, until they are reasonably certain that REXULTI therapy does not adversely affect their ability to engage in such activities [see Warnings and Precautions (5.14)].

Concomitant Medications

Advise patients to inform their healthcare providers of any changes to their current prescription or over-the-counter medications because there is a potential for clinically significant interactions [see Drug Interactions (7.1)].

Pregnancy

Advise patients that third trimester use of REXULTI may cause extrapyramidal and/or withdrawal symptoms in a neonate and to notify their healthcare provider with a known or suspected pregnancy. Advise patients that there is a pregnancy exposure registry that monitors pregnancy outcomes in women exposed to REXULTI during pregnancy [see Use in Specific Populations (8.1)].

Manufactured by Otsuka Pharmaceutical Co., Ltd., Tokyo 101-8535, Japan
Distributed and Marketed by Otsuka America Pharmaceutical, Inc., Rockville, MD 20850 USA
Marketed by Lundbeck, Deerfield, IL 60015 USA

©2025, Otsuka Pharmaceutical Co., Ltd., Tokyo 101-8535, Japan

MEDICATION GUIDE
REXULTI ® (REX-ul-TE)
(brexpiprazole)
tablets, for oral use

What is the most important information I should know about REXULTI?
REXULTI may cause serious side effects, including:

- Increased risk of death in elderly people with dementia-related psychosis. Medicines like REXULTI can raise the risk of death in elderly people who have lost touch with reality (psychosis) due to confusion and memory loss (dementia). REXULTI is not approved for the treatment of people with dementia-related psychosis without agitation that may happen with dementia due to Alzheimer's disease.
- Increased risk of suicidal thoughts and actions. REXULTI and antidepressant medicines increase the risk of suicidal thoughts and actions in people 24 years of age and younger, especially within the first few months of treatment or when the dose is changed.
  - Depression and other mental illnesses are the most important causes of suicidal thoughts and actions.
  How can I watch for and try to prevent suicidal thoughts and actions in myself or a family member?
  - Pay close attention to any changes, especially sudden changes in mood, behaviors, thoughts, or feelings, or if you develop suicidal thoughts or actions. This is very important when REXULTI or the antidepressant medicine is started or when the dose is changed.
  - Call your healthcare provider right away to report new or sudden changes in mood, behavior, thoughts, or feelings, or if you develop suicidal thoughts or actions.
  - Keep all follow-up visits with your healthcare provider as scheduled. Call your healthcare provider between visits as needed, especially if you have concerns about symptoms.
  Call a healthcare provider right away if you or your family member have any of the following symptoms, especially if they are new, worse, or worry you:

- thoughts about suicide or dying
- new or worsening depression
- feeling very agitated or restless
- trouble sleeping (insomnia)
- acting aggressive, being angry, or violent
- an extreme increase in activity or talking (mania)

- attempts to commit suicide
- new or worsening anxiety
- panic attacks
- new or worsening irritability
- acting on dangerous impulses
- other unusual changes in behavior or mood

See "What are the possible side effects of REXULTI?" for more information about side effects.

What is REXULTI?
REXULTI is a prescription medicine used:

- along with antidepressant medicines to treat major depressive disorder (MDD) in adults
- to treat schizophrenia in adults and children ages 13 years and older
- to treat agitation that may happen with dementia due to Alzheimer's disease

REXULTI should not be used as an "as needed" treatment for agitation that may happen with dementia due to Alzheimer's disease.
It is not known if REXULTI is safe and effective for the treatment of MDD in children.
It is not known if REXULTI is safe and effective for the treatment of schizophrenia in children under 13 years of age.

Who should not take REXULTI?
Do not take REXULTI if you are allergic to brexpiprazole or any of the ingredients in REXULTI. See the end of this Medication Guide for a complete list of ingredients in REXULTI.

Before taking REXULTI, tell your healthcare provider about all of your medical conditions, including if you:

- have or have had heart problems or a stroke
- have or have had low or high blood pressure
- have or have had diabetes or high blood sugar or a family history of diabetes or high blood sugar.
- have of have had high levels of total cholesterol, LDL cholesterol, or triglycerides, or low levels of HDL cholesterol
- have or have had seizures (convulsions)
- have or have had kidney or liver problems
- have or have had a low white blood cell count
- are pregnant or plan to become pregnant. REXULTI may harm your unborn baby. Taking REXULTI during your third trimester of pregnancy may cause your baby to have abnormal muscle movements or withdrawal symptoms after birth. Talk to your healthcare provider about the risk to your unborn baby if you take REXULTI during pregnancy.
  - Tell your healthcare provider if you become pregnant or think you are pregnant during treatment with REXULTI.
  - There is a pregnancy exposure registry for women who are exposed to REXULTI during pregnancy. If you become pregnant during treatment with REXULTI, talk to your healthcare provider about registering with the National Pregnancy Registry for Psychiatric Medications. You can register by calling 1-866-961-2388 or visit http://womensmentalhealth.org/clinical-and-research-programs/pregnancyregistry/.
- are breastfeeding or plan to breastfeed. It is not known if REXULTI passes into your breast milk. Talk to your healthcare provider about the best way to feed your baby during treatment with REXULTI.

Tell your healthcare provider about all the medicines you take, including prescription and over-the-counter medicines, vitamins, and herbal supplements.
REXULTI and other medicines may affect each other causing possible serious side effects. REXULTI may affect the way other medicines work, and other medicines may affect how REXULTI works.
Your healthcare provider can tell you if it is safe to take REXULTI with your other medicines. Do not start or stop any medicines during treatment with REXULTI without first talking to your healthcare provider.
Know the medicines you take. Keep a list of them to show your healthcare provider and pharmacist when you get a new medicine.

How should I take REXULTI?

- Take REXULTI exactly as your healthcare provider tells you to take it. Your healthcare provider may change your dose if needed. Do not change the dose or stop taking REXULTI without first talking to your healthcare provider.
- Take REXULTI 1 time each day with or without food.
- If you take too much REXULTI, call your healthcare provider or Poison Help Line at 1-800-222-1222 or go to the nearest hospital emergency room right away.

What should I avoid while taking REXULTI?

- Do not drive a car, operate machinery, or do other dangerous activities until you know how REXULTI affects you. REXULTI may make you feel drowsy.
- Do not become too hot or dehydrated during treatment with REXULTI.
  - Do not exercise too much.
  - In hot weather, stay inside in a cool place if possible.
  - Stay out of the sun.
  - Do not wear too much clothing or heavy clothing.
  - Drink plenty of water.

What are the possible side effects of REXULTI?
REXULTI may cause serious side effects, including:

- See "What is the most important information I should know about REXULTI?"
- Cerebrovascular problems, including stroke, in elderly people with dementia-related psychosis that can lead to death.
- Neuroleptic malignant syndrome (NMS) is a serious condition that can lead to death. Call your healthcare provider or go to the nearest hospital emergency room right away if you have some or all of the following signs and symptoms of NMS:

- high fever
- stiff muscles
- confusion

- changes in your pulse, blood pressure, heart rate, and breathing
- increased sweating

- Uncontrolled body movements (tardive dyskinesia). REXULTI may cause movements that you cannot control in your face, tongue, or other body parts. Tardive dyskinesia may not go away, even if you stop taking REXULTI. Tardive dyskinesia may also start after you stop taking REXULTI.
- Problems with your metabolism such as:
  - high blood sugar (hyperglycemia) and diabetes. Increases in blood sugar can happen in some people who take REXULTI. Extremely high blood sugar can lead to coma or death. Your healthcare provider should check your blood sugar before you start, or soon after you start REXULTI and then regularly during long term treatment with REXULTI.
    Call your healthcare provider if you have any of these symptoms of high blood sugar during treatment with REXULTI:

- feel very thirsty
- feel very hungry
- feel sick to your stomach

- need to urinate more than usual
- feel weak or tired
- feel confused, or your breath smells fruity

- increased fat levels (cholesterol and triglycerides) in your blood. Your healthcare provider should check the fat levels in your blood before you start, or soon after you start REXULTI, and then periodically during treatment with REXULTI.
- weight gain. You and your healthcare provider should check your weight before you start and often during treatment with REXULTI.

- Unusual and uncontrollable (compulsive) urges. Some people taking REXULTI have had strong unusual urges, to gamble and gambling that cannot be controlled (compulsive gambling). Other compulsive urges include sexual urges, shopping, and eating or binge eating. If you or your family members notice that you are having new or unusual strong urges or behaviors, talk to your healthcare provider.
- Low white blood cell count. Your healthcare provider may do blood tests during the first few months of treatment with REXULTI.
- Decreased blood pressure (orthostatic hypotension) and fainting. You may feel dizzy, lightheaded, or pass out (faint) when you rise too quickly from a sitting or lying position.
- Falls. REXULTI may make you sleepy or dizzy, may cause a decrease in your blood pressure when changing position (orthostatic hypotension), and can slow your thinking and motor skills which may lead to falls that can cause fractures or other injuries.
- Seizures (convulsions).
- Problems controlling your body temperature so that you feel too warm. See "What should I avoid while taking REXULTI?"
- Difficulty swallowing that can cause food or liquid to get into your lungs.
- Sleepiness, drowsiness, feeling tired, difficulty thinking and doing normal activities. See "What should I avoid while taking REXULTI?"

The most common side effects of REXULTI in adults include weight gain, sleepiness, dizziness, common cold symptoms, and restlessness or feeling like you need to move (akathisia).
The most common side effects of REXULTI in children 13 to 17 years of age include difficulty moving or slow movement, tremors (shaking), abnormal eye movements, and muscle stiffness.
These are not all the possible side effects of REXULTI.
Call your doctor for medical advice about side effects. You may report side effects to FDA at 1-800-FDA-1088.

How should I store REXULTI?

- Store REXULTI at room temperature between 68°F to 77°F (20°C to 25°C).

Keep REXULTI and all medicines out of the reach of children.

General information about the safe and effective use of REXULTI.
Medicines are sometimes prescribed for purposes other than those listed in a Medication Guide. Do not use REXULTI for a condition for which it was not prescribed. Do not give REXULTI to other people, even if they have the same symptoms you have. It may harm them. You can ask your pharmacist or healthcare provider for information about REXULTI that is written for health professionals.

What are the ingredients in REXULTI?
Active ingredient: brexpiprazole
Inactive ingredients: lactose monohydrate, corn starch, microcrystalline cellulose, hydroxypropyl cellulose, low-substituted hydroxypropyl cellulose, magnesium stearate, hypromellose, and talc
For color: titanium dioxide, iron oxide, and ferrosoferric oxide
Manufactured by Otsuka Pharmaceutical Co., Ltd., Tokyo 101-8535, Japan
Distributed and Marketed by Otsuka America Pharmaceutical, Inc., Rockville, MD 20850 USA
Marketed by Lundbeck, Deerfield, IL 60015 USA
©2025 For more information about REXULTI, go to www.REXULTI.com or call 1-800-441-6763.

This Medication Guide has been approved by the U.S. Food and Drug Administration.

Revised: 5/2025

PRINCIPAL DISPLAY PANEL - 0.25 mg Tablet Bottle Label

0.25 mg

30 Tablets
NDC 59148-035-13

REXULTI®
brexpiprazole
tablets

Rx only

Keep out of the reach of children

DISPENSE THE
ACCOMPANYING
MEDICATION GUIDE
TO EACH PATIENT

Otsuka

Lundbeck

PRINCIPAL DISPLAY PANEL - 0.25 mg Tablet Bottle Carton

0.25 mg

30 Tablets
NDC 59148-035-13

REXULTI®
brexpiprazole
tablets

Rx only

Keep out of the
reach of children

DISPENSE THE
ACCOMPANYING
MEDICATION GUIDE
TO EACH PATIENT

PRINCIPAL DISPLAY PANEL - 0.5 mg Tablet Bottle Label

0.5 mg

30 Tablets
NDC 59148-036-13

REXULTI®
brexpiprazole
tablets

Rx only

Keep out of the reach of children

DISPENSE THE
ACCOMPANYING
MEDICATION GUIDE
TO EACH PATIENT

Otsuka

Lundbeck

PRINCIPAL DISPLAY PANEL - 0.5 mg Tablet Bottle Carton

0.5 mg

30 Tablets
NDC 59148-036-13

REXULTI®
brexpiprazole
tablets

Rx only

Keep out of the
reach of children

DISPENSE THE
ACCOMPANYING
MEDICATION GUIDE
TO EACH PATIENT

PRINCIPAL DISPLAY PANEL - 1 mg Tablet Bottle Label

1 mg

30 Tablets
NDC 59148-037-13

REXULTI®
brexpiprazole
tablets

Rx only

Keep out of the reach of children

DISPENSE THE
ACCOMPANYING
MEDICATION GUIDE
TO EACH PATIENT

Otsuka

Lundbeck

PRINCIPAL DISPLAY PANEL - 1 mg Tablet Bottle Carton

1 mg

30 Tablets
NDC 59148-037-13

REXULTI®
brexpiprazole
tablets

Rx only

Keep out of the
reach of children

DISPENSE THE
ACCOMPANYING
MEDICATION GUIDE
TO EACH PATIENT

PRINCIPAL DISPLAY PANEL - 2 mg Tablet Bottle Label

2 mg

30 Tablets
NDC 59148-038-13

REXULTI®
brexpiprazole
tablets

Rx only

Keep out of the reach of children

DISPENSE THE
ACCOMPANYING
MEDICATION GUIDE
TO EACH PATIENT

Otsuka

Lundbeck

PRINCIPAL DISPLAY PANEL - 2 mg Tablet Bottle Carton

2 mg

30 Tablets
NDC 59148-038-13

REXULTI®
brexpiprazole
tablets

Rx only

Keep out of the
reach of children

DISPENSE THE
ACCOMPANYING
MEDICATION GUIDE
TO EACH PATIENT

PRINCIPAL DISPLAY PANEL - 3 mg Tablet Bottle Label

3 mg

30 Tablets
NDC 59148-039-13

REXULTI®
brexpiprazole
tablets

Rx only

Keep out of the reach of children

DISPENSE THE
ACCOMPANYING
MEDICATION GUIDE
TO EACH PATIENT

Otsuka

Lundbeck

PRINCIPAL DISPLAY PANEL - 3 mg Tablet Bottle Carton

3 mg

30 Tablets
NDC 59148-039-13

REXULTI®
brexpiprazole
tablets

Rx only

Keep out of the
reach of children

DISPENSE THE
ACCOMPANYING
MEDICATION GUIDE
TO EACH PATIENT

PRINCIPAL DISPLAY PANEL - 4 mg Tablet Bottle Label

4 mg

30 Tablets
NDC 59148-040-13

REXULTI®
brexpiprazole
tablets

Rx only

Keep out of the reach of children

DISPENSE THE
ACCOMPANYING
MEDICATION GUIDE
TO EACH PATIENT

Otsuka

Lundbeck

PRINCIPAL DISPLAY PANEL - 4 mg Tablet Bottle Carton

4 mg

30 Tablets
NDC 59148-040-13

REXULTI®
brexpiprazole
tablets

Rx only

Keep out of the
reach of children

DISPENSE THE
ACCOMPANYING
MEDICATION GUIDE
TO EACH PATIENT